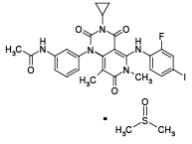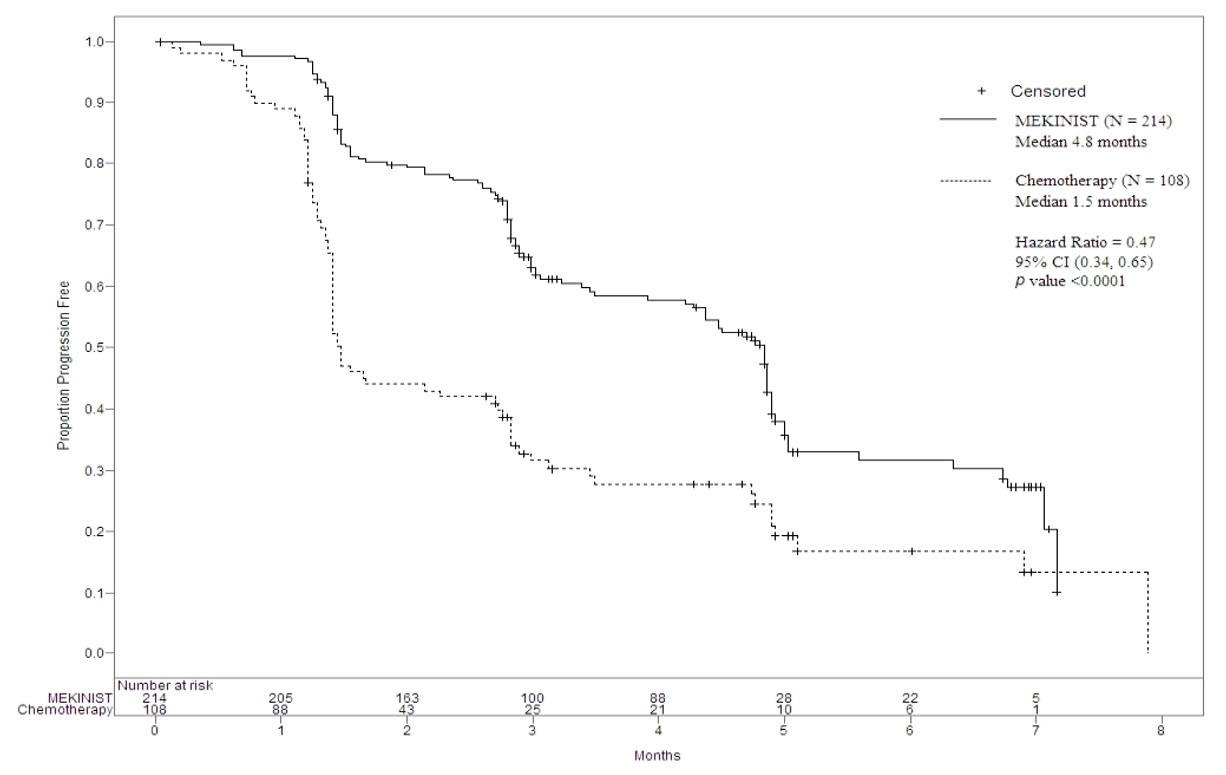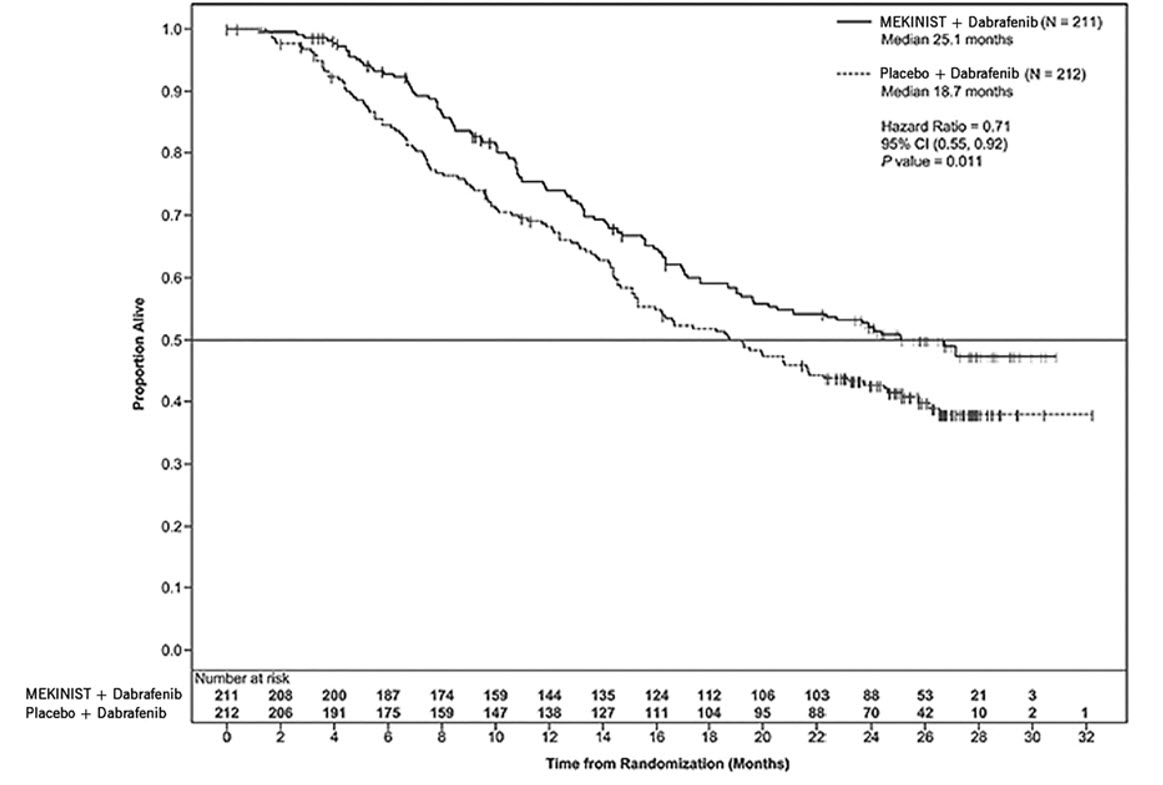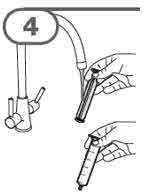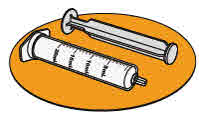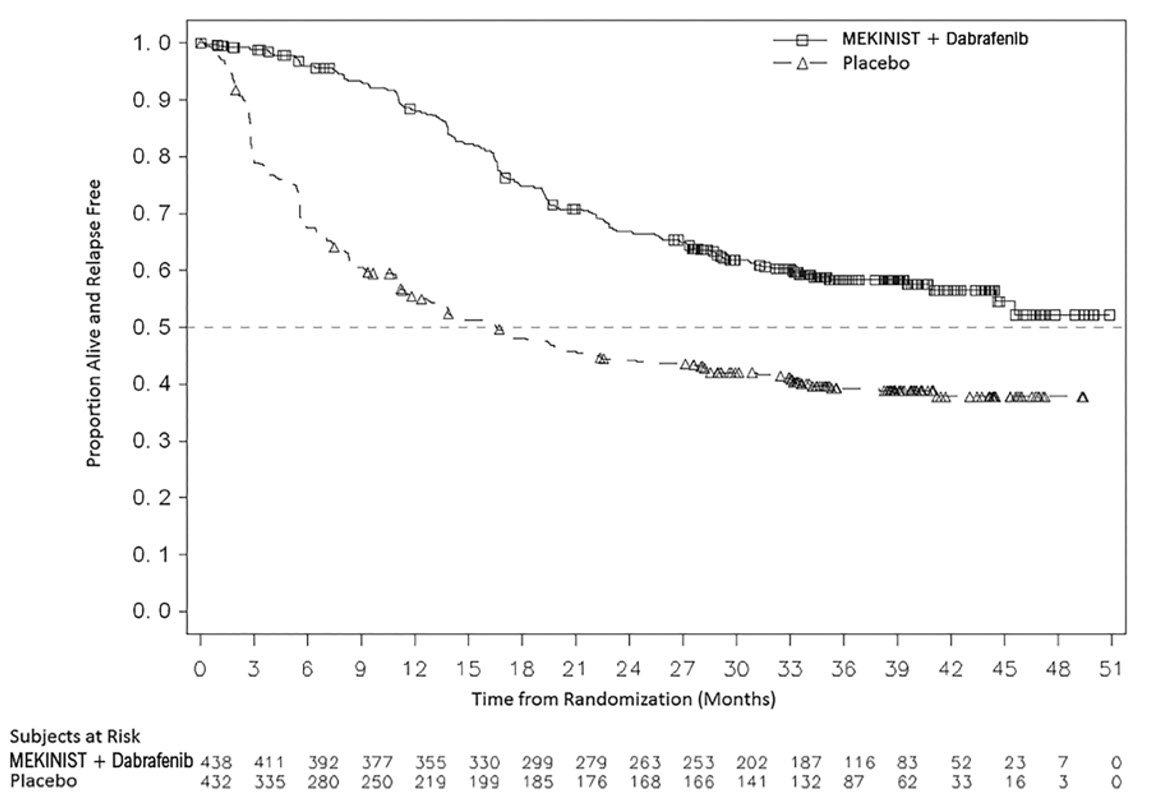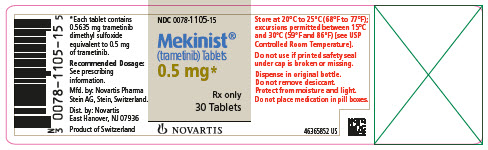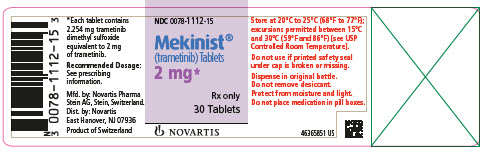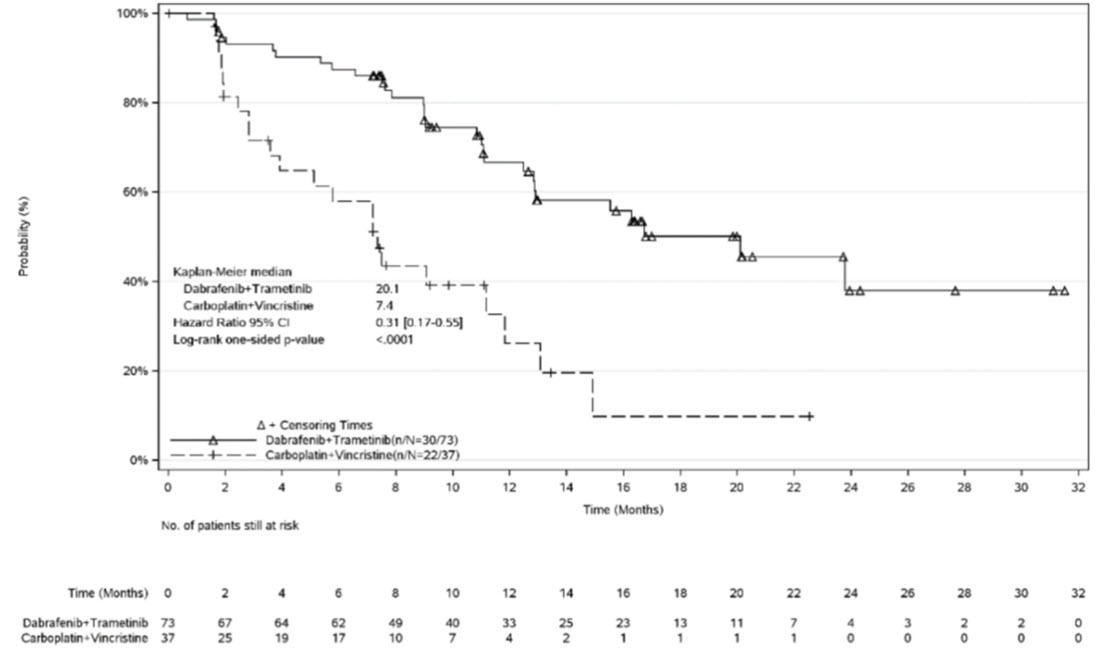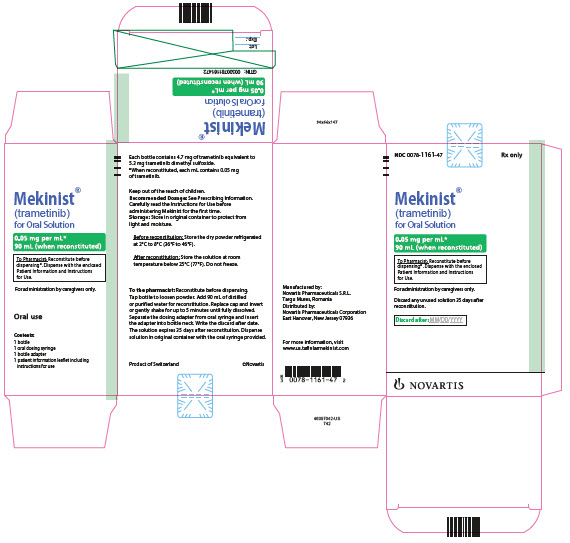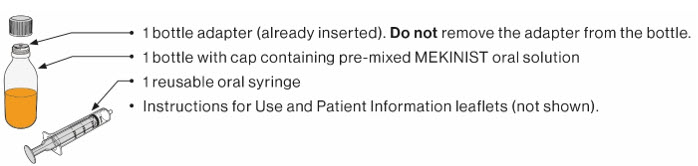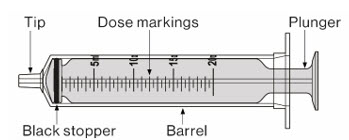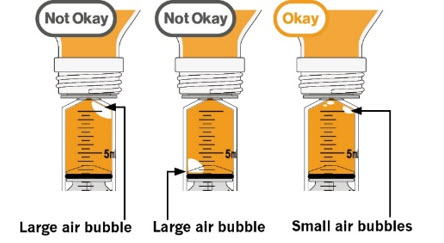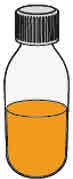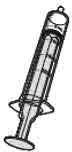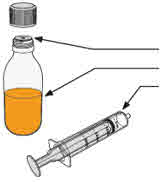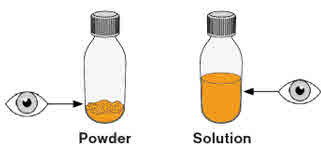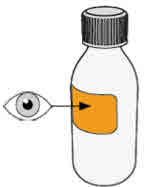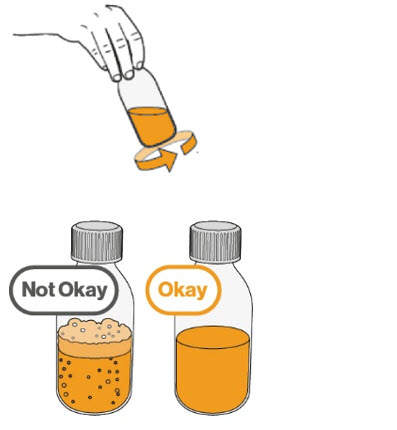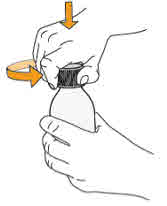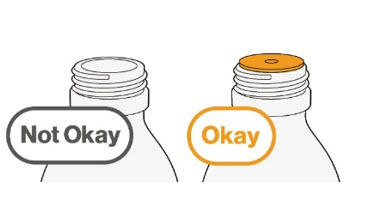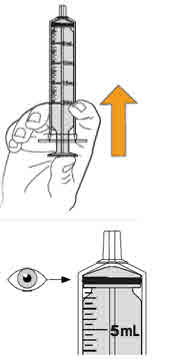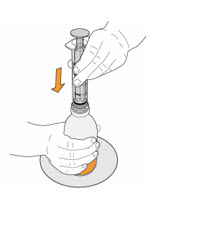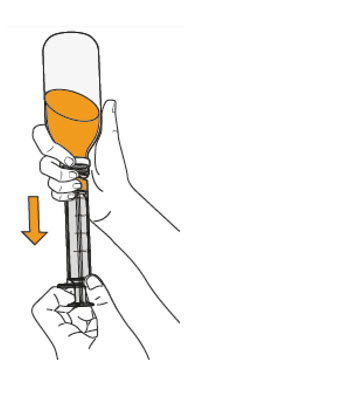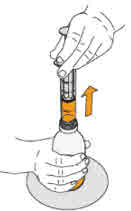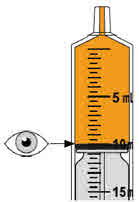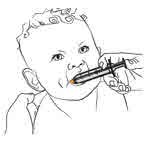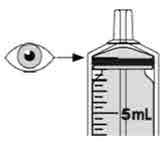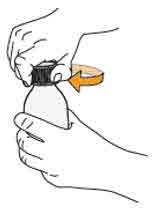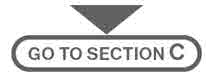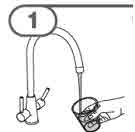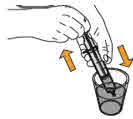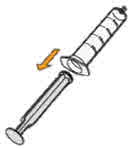 DRUG LABEL: Mekinist
NDC: 0078-1105 | Form: TABLET, FILM COATED
Manufacturer: Novartis Pharmaceuticals Corporation
Category: prescription | Type: HUMAN PRESCRIPTION DRUG LABEL
Date: 20260127

ACTIVE INGREDIENTS: TRAMETINIB DIMETHYL SULFOXIDE .5 mg/1 1
INACTIVE INGREDIENTS: SILICON DIOXIDE; CROSCARMELLOSE SODIUM; HYPROMELLOSES; MAGNESIUM STEARATE; MANNITOL; MICROCRYSTALLINE CELLULOSE; SODIUM LAURYL SULFATE; FERRIC OXIDE YELLOW; POLYETHYLENE GLYCOL; TITANIUM DIOXIDE

HIGHLIGHTS OF PRESCRIBING INFORMATION

These highlights do not include all the information needed to use MEKINIST safely and effectively. See full prescribing information for MEKINIST.
MEKINIST® (trametinib) tablets, for oral use
MEKINIST® (trametinib) for oral solution
Initial U.S. Approval: 2013

RECENT MAJOR CHANGES

Indications and Usage, BRAF V600E Mutation-Positive Locally Advanced or Metastatic Anaplastic Thyroid Cancer (1.4) | 1/2025
Dosage and Administration, Patient Selection (2.1) | 1/2025
Dosage and Administration, Administration (2.3) | 3/2025

1 INDICATIONS AND USAGE

MEKINIST is a kinase inhibitor indicated as a single agent for the treatment of BRAF-inhibitor treatment-naïve patients with unresectable or metastatic melanoma with BRAF V600E or V600K mutations as detected by an FDA-approved test. (1.1, 2.1)

MEKINIST is indicated, in combination with dabrafenib, for:

- the treatment of patients with unresectable or metastatic melanoma with BRAF V600E or V600K mutations as detected by an FDA-approved test. (1.1, 2.1)
- the adjuvant treatment of patients with melanoma with BRAF V600E or V600K mutations, as detected by an FDA-approved test, and involvement of lymph node(s), following complete resection. (1.2, 2.1)
- the treatment of patients with metastatic non-small cell lung cancer (NSCLC) with BRAF V600E mutation as detected by an FDA-approved test. (1.3, 2.1)
- the treatment of patients with locally advanced or metastatic anaplastic thyroid cancer (ATC) with BRAF V600E mutation, as detected by an FDA-approved test, and with no satisfactory locoregional treatment options. (1.4, 2.1)
- the treatment of adult and pediatric patients 1 year of age and older with unresectable or metastatic solid tumors with BRAF V600E mutation who have progressed following prior treatment and have no satisfactory alternative treatment options. This indication is approved under accelerated approval based on overall response rate and duration of response. Continued approval for this indication may be contingent upon verification and description of clinical benefit in a confirmatory trial(s). (1.5, 2.1)
- the treatment of pediatric patients 1 year of age and older with low-grade glioma (LGG) with a BRAF V600E mutation who require systemic therapy. (1.6, 2.1)

Limitations of Use: MEKINIST is not indicated for treatment of patients with colorectal cancer because of known intrinsic resistance to BRAF inhibition. (1.7, 12.1)

2 DOSAGE AND ADMINISTRATION

- The recommended dosage of MEKINIST in adult patients is 2 mg orally once daily. The recommended dosage for MEKINIST in pediatric patients is based on body weight. (2)

3 DOSAGE FORMS AND STRENGTHS

MEKINIST Tablets: 0.5 mg, 2 mg (3)

MEKINIST for Oral Solution: 4.7 mg (3)

4 CONTRAINDICATIONS

None. (4)

5 WARNINGS AND PRECAUTIONS

- New Primary Malignancies, Cutaneous and Non-Cutaneous: Can occur when MEKINIST is used with dabrafenib. Monitor patients for new malignancies prior to, or while on therapy, and following discontinuation of treatment. (5.1)
- Hemorrhage: Major hemorrhagic events can occur. Monitor for signs and symptoms of bleeding. (5.2)
- Colitis and Gastrointestinal Perforation: Colitis and gastrointestinal perforation can occur in patients receiving MEKINIST. (5.3)
- Venous Thromboembolic Events: Deep vein thrombosis (DVT) and pulmonary embolism (PE) can occur in patients receiving MEKINIST. (5.4, 2.4)
- Cardiomyopathy: Assess left ventricular ejection fraction (LVEF) before treatment, after one month of treatment, then every 2 to 3 months thereafter. (5.5, 2.4)
- Ocular Toxicities: Perform ophthalmological evaluation for any visual disturbances. For Retinal Vein Occlusion (RVO), permanently discontinue MEKINIST. (5.6, 2.4)
- Interstitial Lung Disease (ILD)/Pneumonitis: Withhold MEKINIST for new or progressive unexplained pulmonary symptoms. Permanently discontinue MEKINIST for treatment-related ILD or pneumonitis. (5.7, 2.4)
- Serious Febrile Reactions: Can occur when MEKINIST is used with dabrafenib. (5.8, 2.4)
- Serious Skin Toxicities: Monitor for skin toxicities and for secondary infections. Permanently discontinue MEKINIST for intolerable Grade 2 or for Grade 3 or 4 rash not improving within 3 weeks despite interruption of MEKINIST. Permanently discontinue for severe cutaneous adverse reactions (SCARs). (5.9, 2.4)
- Hyperglycemia: Monitor serum glucose levels in patients with preexisting diabetes or hyperglycemia. (5.10)
- Hemophagocytic Lymphohistiocytosis (HLH): Interrupt treatment for suspected HLH. Discontinue treatment if HLH is confirmed. (5.12)
- Embryo-Fetal Toxicity: Can cause fetal harm. Advise females of reproductive potential of potential risk to a fetus and to use effective contraception. (5.13, 8.1, 8.3)

6 ADVERSE REACTIONS

Most common adverse reactions (≥ 20%) for MEKINIST as a single agent include rash, diarrhea, and lymphedema. (6.1)

Most common adverse reactions (≥ 20%) for MEKINIST in combination with dabrafenib include:

- Unresectable or metastatic melanoma: pyrexia, nausea, rash, chills, diarrhea, vomiting, hypertension, and peripheral edema. (6.1)
- Adjuvant treatment of melanoma: pyrexia, fatigue, nausea, headache, rash, chills, diarrhea, vomiting, arthralgia, and myalgia. (6.1)
- NSCLC: pyrexia, fatigue, nausea, vomiting, diarrhea, dry skin, decreased appetite, edema, rash, chills, hemorrhage, cough, and dyspnea. (6.1)
- Adult patients with solid tumors: pyrexia, fatigue, nausea, rash, chills, headache, hemorrhage, cough, vomiting, constipation, diarrhea, myalgia, arthralgia, and edema. (6.1)
- Pediatric patients with solid tumors: pyrexia, rash, vomiting, fatigue, dry skin, cough, diarrhea, dermatitis acneiform, headache, abdominal pain, nausea, hemorrhage, constipation, and paronychia. (6.1)
- Pediatric patients with LGG: pyrexia, rash, headache, vomiting, musculoskeletal pain, fatigue, diarrhea, dry skin, nausea, hemorrhage, abdominal pain, and dermatitis acneiform. (6.1)

To report SUSPECTED ADVERSE REACTIONS, contact Novartis Pharmaceuticals Corporation at 1-888-669-6682 or FDA at 1-800-FDA-1088 or www.fda.gov/medwatch.

8 USE IN SPECIFIC POPULATIONS

- Lactation: Do not breastfeed. (8.2)
- Females and Males of Reproductive Potential: May impair fertility. Counsel patients on pregnancy planning and prevention. (8.3)

FULL PRESCRIBING INFORMATION

1 INDICATIONS AND USAGE

1.1 BRAF V600E or V600K Mutation-Positive Unresectable or Metastatic Melanoma

MEKINIST® is indicated, as a single agent in BRAF-inhibitor treatment-naïve patients or in combination with dabrafenib, for the treatment of patients with unresectable or metastatic melanoma with BRAF V600E or V600K mutations, as detected by an FDA-approved test [see Dosage and Administration (2.1)].

1.2 Adjuvant Treatment of BRAF V600E or V600K Mutation-Positive Melanoma

MEKINIST is indicated, in combination with dabrafenib, for the adjuvant treatment of patients with melanoma with BRAF V600E or V600K mutations as detected by an FDA-approved test, and involvement of lymph node(s), following complete resection [see Dosage and Administration (2.1)].

1.3 BRAF V600E Mutation-Positive Metastatic NSCLC

MEKINIST is indicated, in combination with dabrafenib, for the treatment of patients with metastatic non-small cell lung cancer (NSCLC) with BRAF V600E mutation as detected by an FDA-approved test [see Dosage and Administration (2.1)].

1.4 BRAF V600E Mutation-Positive Locally Advanced or Metastatic Anaplastic Thyroid Cancer

MEKINIST is indicated, in combination with dabrafenib, for the treatment of patients with locally advanced or metastatic anaplastic thyroid cancer (ATC) with BRAF V600E mutation, as detected by an FDA-approved test, and with no satisfactory locoregional treatment options [see Dosage and Administration (2.1)].

1.5 BRAF V600E Mutation-Positive Unresectable or Metastatic Solid Tumors

MEKINIST is indicated, in combination with dabrafenib, for the treatment of adult and pediatric patients 1 year of age and older with unresectable or metastatic solid tumors with BRAF V600E mutation who have progressed following prior treatment and have no satisfactory alternative treatment options [see Dosage and Administration (2.1)]. This indication is approved under accelerated approval based on overall response rate and duration of response [see Clinical Studies (14.6)]. Continued approval for this indication may be contingent upon verification and description of clinical benefit in a confirmatory trial(s).

1.6 BRAF V600E Mutation-Positive Low-Grade Glioma

MEKINIST is indicated, in combination with dabrafenib, for the treatment of pediatric patients 1 year of age and older with low-grade glioma (LGG) with a BRAF V600E mutation who require systemic therapy [see Dosage and Administration (2.1)].

1.7 Limitations of Use

MEKINIST is not indicated for treatment of patients with colorectal cancer because of known intrinsic resistance to BRAF inhibition [see Indications and Usage (1.5), Clinical Pharmacology (12.1)].

2 DOSAGE AND ADMINISTRATION

2.1 Patient Selection

Melanoma

- Confirm the presence of BRAF V600E or V600K mutation in tumor specimens prior to initiation of treatment with MEKINIST as a single agent or in combination with dabrafenib [see Clinical Studies (14.1, 14.2)].
- Information on FDA-approved tests for the detection of BRAF V600 mutations in melanoma is available at: http://www.fda.gov/CompanionDiagnostics.

NSCLC

- Confirm the presence of BRAF V600E mutation in tumor specimens prior to initiation of treatment with MEKINIST and dabrafenib [see Clinical Studies (14.3)].
- Information on FDA-approved tests for the detection of BRAF V600E mutations in NSCLC is available at: http://www.fda.gov/CompanionDiagnostics.

ATC

- Confirm the presence of BRAF V600E mutation in tumor specimens prior to initiation of treatment with MEKINIST and dabrafenib [see Clinical Studies (14.4)].
- Information on FDA-approved tests for the detection of BRAF V600E mutations in ATC is available at: http://www.fda.gov/CompanionDiagnostics.

Solid Tumors

- Confirm the presence of BRAF V600E mutation in tumor specimens prior to initiation of treatment with MEKINIST and dabrafenib [see Clinical Studies (14.6)]. An FDA-approved test for the detection of BRAF V600E mutation in solid tumors other than melanoma and NSCLC is not currently available.

Low-Grade Glioma

- Confirm the presence of BRAF V600E mutation in tumor specimens prior to initiation of treatment with MEKINIST and dabrafenib [see Clinical Studies (14.7)]. An FDA-approved test for the detection of BRAF V600E mutation in LGG is not currently available.

2.2 Recommended Dosage

MEKINIST Tablets

Adult Patients

The recommended dosage for MEKINIST tablets in adult patients is 2 mg orally taken once daily [see Dosage and Administration (2.3)].

Pediatric Patients

The recommended dosage for MEKINIST tablets in pediatric patients who weigh at least 26 kg is based on body weight (Table 1) [see Dosage and Administration (2.3)]. A recommended dosage of MEKINIST tablets has not been established in patients who weigh less than 26 kg.

Table 1. Recommended Dosage for MEKINIST Tablets in Pediatric Patients (Weight-based)
Body Weight | Recommended Dosage
26 to 37 kg | 1 mg orally once daily
38 to 50 kg | 1.5 mg orally once daily
51 kg or greater | 2 mg orally once daily

MEKINIST for Oral Solution

Adult and Pediatric Patients

The recommended dosage for MEKINIST for oral solution for adult and pediatric patients is based on body weight (Table 2) [see Dosage and Administration (2.3)].

Table 2. Recommended Dosage for MEKINIST for Oral Solution in Adult and Pediatric Patients (Weight-based)
Body Weight | Recommended Dosage Total Volume of Oral Solution Once Daily (Trametinib Content)
8 kg | 0.3 mg (6 mL)
9 kg | 0.35 mg (7 mL)
10 kg | 0.35 mg (7 mL)
11 kg | 0.4 mg (8 mL)
12 to 13 kg | 0.45 mg (9 mL)
14 to 17 kg | 0.55 mg (11 mL)
18 to 21 kg | 0.7 mg (14 mL)
22 to 25 kg | 0.85 mg (17 mL)
26 to 29 kg | 0.9 mg (18 mL)
30 to 33 kg | 1 mg (20 mL)
34 to 37 kg | 1.15 mg (23 mL)
38 to 41 kg | 1.25 mg (25 mL)
42 to 45 kg | 1.4 mg (28 mL)
46 to 50 kg | 1.6 mg (32 mL)
≥ 51 kg | 2 mg (40 mL)

Duration of Treatment

- The recommended duration of treatment for patients with unresectable or metastatic melanoma or solid tumors, metastatic NSCLC, or locally advanced or metastatic anaplastic thyroid cancer is until disease progression or unacceptable toxicity.
- The recommended duration of treatment in the adjuvant melanoma setting is until disease recurrence or unacceptable toxicity for up to 1 year.
- The recommended duration of treatment for pediatric patients with LGG is until disease progression or until unacceptable toxicity.

Combination Therapy with Dabrafenib

Refer to the dabrafenib prescribing information for recommended dabrafenib dosing information.

2.3 Administration

- Take MEKINIST at the same time each day, approximately 24 hours apart.
- Do not take a missed dose of MEKINIST within 12 hours of the next dose of MEKINIST.
- If vomiting occurs after MEKINIST administration, do not take an additional dose. Take the next dose at its scheduled time.

MEKINIST Tablets

- Take MEKINIST tablets on an empty stomach (at least 1 hour before or 2 hours after a meal) [see Clinical Pharmacology (12.3)].
- Do not crush or break MEKINIST tablets.

MEKINIST for Oral Solution

- MEKINIST powder for oral solution must be reconstituted by a pharmacist or other healthcare provider prior to dispensing to the patient.
- MEKINIST for oral solution is intended for administration by a caregiver. Prior to use of the oral solution, ensure caregivers receive training on proper dosing and administration of MEKINIST for oral solution.
- When administering MEKINIST for oral solution as a single agent, take the oral solution with a low-fat meal or on an empty stomach [see Clinical Pharmacology (12.3)].
- When coadministering with dabrafenib, take the MEKINIST oral solution on an empty stomach (at least 1 hour before or 2 hours after a meal). Breastfeeding and/or baby formula may be given on demand if a pediatric patient is unable to tolerate the fasting conditions [see Clinical Pharmacology (12.3)].

Preparation and Administration

- To prepare MEKINIST for oral solution, tap the bottle until powder flows freely. Add 90 mL distilled or purified water to the powder in the bottle and invert or gently shake the bottle with re-attached cap for up to 5 minutes until powder is fully dissolved yielding a clear solution. Separate the bottle adapter from the oral syringe. Insert bottle adapter into bottle neck after reconstitution of the solution. Write the discard after date. Once reconstituted, MEKINIST for oral solution can be used for 35 days.
- The final concentration of the solution is 0.05 mg/mL.
- Administer MEKINIST for oral solution from an oral syringe or feeding tube (4 French gauge or larger).
- After reconstitution, store in original bottle below 25°C (77°F) and do not freeze.

2.4 Dosage Modifications for Adverse Reactions

Dose reductions for adverse reactions associated with MEKINIST are presented in Tables 3 and 4.

Table 3. Recommended Dosage Reductions for MEKINIST Tablets for Adverse Reactions
Recommended Dosage | 1 mg orally once daily | 1.5 mg orally once daily | 2 mg orally once daily
First dose reduction | 0.5 mg orally once daily | 1 mg orally once daily | 1.5 mg orally once daily
Second dose reduction | N/A | 0.5 mg orally once daily | 1 mg orally once daily
Subsequent modification | Permanently discontinue MEKINIST tablets if unable to tolerate a maximum of two dose reductions.

Table 4. Recommended Dosage Reductions for MEKINIST for Oral Solution for Adverse Reactions
Body Weight (Recommended dosage once daily) | First Dose Reduction (Administer once daily) | Second Dose Reduction (Administer once daily)
8 kg [0.3 mg (6 mL)] | 0.25 mg (5 mL) | 0.15 mg (3 mL)
9 kg [0.35 mg (7 mL)] | 0.25 mg (5 mL) | 0.2 mg (4 mL)
10 kg [0.35 mg (7 mL)] | 0.25 mg (5 mL) | 0.2 mg (4 mL)
11 kg [0.4 mg (8 mL)] | 0.3 mg (6 mL) | 0.2 mg (4 mL)
12 to 13 kg [0.45 mg (9 mL)] | 0.35 mg (7 mL) | 0.25 mg (5 mL)
14 to 17 kg [0.55 mg (11 mL)] | 0.4 mg (8 mL) | 0.3 mg (6 mL)
18 to 21 kg [0.7 mg (14 mL)] | 0.55 mg (11 mL) | 0.35 mg (7 mL)
22 to 25 kg [0.85 mg (17 mL)] | 0.65 mg (13 mL) | 0.45 mg (9 mL)
26 to 29 kg [0.9 mg (18 mL)] | 0.7 mg (14 mL) | 0.45 mg (9 mL)
30 to 33 kg [1 mg (20 mL)] | 0.75 mg (15 mL) | 0.5 mg (10 mL)
34 to 37 kg [1.15 mg (23 mL)] | 0.85 mg (17 mL) | 0.6 mg (12 mL)
38 to 41 kg [1.25 mg (25 mL)] | 0.95 mg (19 mL) | 0.65 mg (13 mL)
42 to 45 kg [1.4 mg (28 mL)] | 1.05 mg (21 mL) | 0.7 mg (14 mL)
46 to 50 kg [1.6 mg (32 mL)] | 1.2 mg (24 mL) | 0.8 mg (16 mL)
≥ 51 kg [2 mg (40 mL)] | 1.5 mg (30 mL) | 1 mg (20 mL)
Permanently discontinue MEKINIST for oral solution if unable to tolerate a maximum of two dose reductions.

Dosage modifications for adverse reactions associated with MEKINIST are presented in Table 5.

Table 5. Recommended Dosage Modifications for MEKINIST for Adverse Reactions
Severity of Adverse Reactiona | Dosage Modification for MEKINISTb
Hemorrhage [see Warnings and Precautions (5.2)]
- Grade 3 | Withhold MEKINIST.; - If improved, resume MEKINIST at lower dose. - If not improved, permanently discontinue MEKINIST.
- Grade 4 | Permanently discontinue MEKINIST.
Venous Thromboembolic Events [see Warnings and Precautions (5.4)]
- Uncomplicated deep venous thrombosis (DVT) or pulmonary embolism (PE) | Withhold MEKINIST for up to 3 weeks.; - If improved to Grade 0-1, resume MEKINIST at lower dose. - If not improved, permanently discontinue MEKINIST.
- Life-threatening PE | Permanently discontinue MEKINIST.
Cardiomyopathy [see Warnings and Precautions (5.5)]
- Asymptomatic, absolute decrease in left ventricular ejection fraction (LVEF) of 10% or greater from baseline that is below the institutional lower limit of normal (LLN) | Withhold MEKINIST for up to 4 weeks.; - If improved to normal LVEF value, resume MEKINIST at lower dose. - If not improved to normal LVEF value, permanently discontinue MEKINIST.
- Symptomatic cardiomyopathy - Absolute decrease in LVEF of greater than 20% from baseline that is below the institutional LLN | Permanently discontinue MEKINIST.
Ocular Toxicities [see Warnings and Precautions (5.6)]
- Retinal pigment epithelial detachments (RPED) | Withhold MEKINIST for up to 3 weeks.; - If improved, resume MEKINIST at same or lower dose. - If not improved, permanently discontinue MEKINIST or resume MEKINIST at lower dose.
- Retinal vein occlusion (RVO) | Permanently discontinue MEKINIST.
Pulmonary [see Warnings and Precautions (5.7)]
- Interstitial lung disease (ILD)/pneumonitis | Permanently discontinue MEKINIST.
Febrile Reactions [see Warnings and Precautions (5.8)]
- Fever of 100.4°F to 104°F (or first symptoms in case of recurrence) | Withhold MEKINIST until fever resolves, then resume MEKINIST at same or lower dose.
- Fever higher than 104°F - Fever complicated by rigors, hypotension, dehydration, or renal failure | - Withhold MEKINIST until febrile reactions resolve for at least 24 hours, then resume MEKINIST at lower dose.; Or; - Permanently discontinue MEKINIST.
Skin Toxicities [see Warnings and Precautions (5.9)]
- Intolerable Grade 2 - Grade 3 or 4 | Withhold MEKINIST for up to 3 weeks.; - If improved, resume MEKINIST at lower dose. - If not improved, permanently discontinue MEKINIST.
- Severe cutaneous adverse reactions (SCARs) | Permanently discontinue MEKINIST.
Other Adverse Reactionsc
- Intolerable Grade 2 - Any Grade 3 | Withhold MEKINIST.; - If improved to Grade 0-1, resume MEKINIST at lower dose. - If not improved, permanently discontinue MEKINIST.
- First occurrence of any Grade 4 | - Withhold MEKINIST until improves to Grade 0-1, then resume MEKINIST at lower dose.; Or; - Permanently discontinue MEKINIST.
- Recurrent Grade 4 | Permanently discontinue MEKINIST.
aNational Cancer Institute Common Terminology Criteria for Adverse Events (NCI CTCAE) version 4.0.
bSee Tables 3 and 4 for recommended dose reductions of MEKINIST.
cDose modifications are not recommended for MEKINIST when administered with dabrafenib for the following adverse reactions of dabrafenib: non-cutaneous malignancies and uveitis. Dose modification of MEKINIST is not required for new primary cutaneous malignancies.

Refer to the dabrafenib prescribing information for dose modifications for adverse reactions associated with dabrafenib.

3 DOSAGE FORMS AND STRENGTHS

MEKINIST tablets:

- 0.5 mg tablets: Yellow, ovaloid, biconvex, unscored film-coated tablets with beveled edges and with the Novartis logo debossed on one side and ‘TT’ on the other side.
- 2 mg tablets: Pink, round, biconvex, unscored film-coated tablets with beveled edges and with the Novartis logo debossed on one side and ‘LL’ on the other side.

MEKINIST for oral solution:

- White to almost white powder containing 4.7 mg of trametinib per bottle. Each mL of reconstituted strawberry-flavored trametinib solution contains 0.05 mg of trametinib.

4 CONTRAINDICATIONS

None.

5 WARNINGS AND PRECAUTIONS

5.1 New Primary Malignancies

Cutaneous Malignancies

MEKINIST Administered with Dabrafenib (Adult): In the pooled safety population [see Adverse Reactions (6.1)], cutaneous squamous cell carcinomas (cuSCCs) and keratoacanthomas occurred in 2% of patients. Basal cell carcinoma and new primary melanoma occurred in 3% and < 1% of patients, respectively.

MEKINIST Administered with Dabrafenib (Pediatric): In the pooled safety population, new primary melanoma occurred in < 1% of patients.

Perform dermatologic evaluations prior to initiation of MEKINIST when used with dabrafenib, every 2 months while on therapy, and for up to 6 months following discontinuation of the combination.

Non-Cutaneous Malignancies

Based on its mechanism of action, dabrafenib may promote growth and development of malignancies with activation of RAS through mutation or other mechanisms; refer to the prescribing information for dabrafenib.

In the pooled safety population of MEKINIST administered with dabrafenib, non-cutaneous malignancies occurred in 1% of patients.

Monitor patients receiving MEKINIST and dabrafenib closely for signs or symptoms of non-cutaneous malignancies. No dose modification is required for MEKINIST in patients who develop non-cutaneous malignancies.

5.2 Hemorrhage

Hemorrhages, including major hemorrhage defined as symptomatic bleeding in a critical area or organ, can occur with MEKINIST. Fatal cases have been reported.

MEKINIST Administered with Dabrafenib (Adult): In the pooled safety population [see Adverse Reactions (6.1)], hemorrhagic events occurred in 17% of patients; gastrointestinal hemorrhage occurred in 3% of patients; intracranial hemorrhage occurred in 0.6% of patients; fatal hemorrhage occurred in 0.5% of patients. The fatal events were cerebral hemorrhage and brainstem hemorrhage.

MEKINIST Administered with Dabrafenib (Pediatric): In the pooled safety population, hemorrhagic events occurred in 25% of patients; the most common type of bleeding was epistaxis (16%). Serious events of bleeding occurred in 3.6% of patients and included gastrointestinal hemorrhage (1.2%), cerebral hemorrhage (0.6%), uterine hemorrhage (0.6%), post-procedural hemorrhage (0.6%), and epistaxis (0.6%).

Permanently discontinue MEKINIST for all Grade 4 hemorrhagic events and for any Grade 3 hemorrhagic events that do not improve. Withhold MEKINIST for Grade 3 hemorrhagic events; if improved, resume MEKINIST at the next lower dose level.

5.3 Colitis and Gastrointestinal Perforation

Colitis and gastrointestinal perforation, including fatal outcomes, have been reported in patients taking:

MEKINIST Monotherapy and Administered with Dabrafenib (Adult): In the pooled safety population [see Adverse Reactions (6.1)], colitis occurred in < 1% of patients and gastrointestinal perforation occurred in < 1% of patients.

MEKINIST Administered with Dabrafenib (Pediatric): In the pooled safety population, colitis events occurred in < 1% of patients.

Monitor patients closely for colitis and gastrointestinal perforations.

5.4 Venous Thromboembolic Events

MEKINIST Administered with Dabrafenib (Adult): In the pooled safety population [see Adverse Reactions (6.1)], deep vein thrombosis (DVT) and pulmonary embolism (PE) occurred in 2% of patients.

MEKINIST Administered with Dabrafenib (Pediatric): In the pooled safety population, embolism events occurred in < 1% of patients.

Advise patients to immediately seek medical care if they develop symptoms of DVT or PE, such as shortness of breath, chest pain, or arm or leg swelling. Permanently discontinue MEKINIST for life-threatening PE. Withhold MEKINIST for uncomplicated DVT and PE for up to 3 weeks; if improved, MEKINIST may be resumed at a lower dose level [see Dosage and Administration (2.4)].

5.5 Cardiomyopathy

Cardiomyopathy, including cardiac failure, can occur with MEKINIST.

MEKINIST Administered with Dabrafenib (Adult): In the pooled safety population [see Adverse Reactions (6.1)], cardiomyopathy, defined as a decrease in left ventricular ejection fraction (LVEF) ≥ 10% from baseline and below the institutional lower limit of normal (LLN), occurred in 6% of patients. Development of cardiomyopathy resulted in dose interruption or discontinuation of MEKINIST in 3% and < 1% of patients, respectively. Cardiomyopathy resolved in 45 of 50 patients who received MEKINIST administered with dabrafenib.

MEKINIST Administered with Dabrafenib (Pediatric): In the pooled safety population, cardiomyopathy, defined as a decrease in LVEF ≥ 10% from baseline and below the institutional LLN, occurred in 9% of patients.

Assess LVEF by echocardiogram or multigated acquisition (MUGA) scan before initiation of MEKINIST as a single agent or with dabrafenib, one month after initiation, and then at 2- to 3-month intervals while on treatment. For an asymptomatic absolute decrease in LVEF of 10% or greater from baseline that is below the institutional LLN, withhold MEKINIST for up to 4 weeks. If improved to normal LVEF value, resume MEKINIST at a lower dose. If no improvement to normal LVEF value within 4 weeks, permanently discontinue MEKINIST. For symptomatic cardiomyopathy or an absolute decrease in LVEF of greater than 20% from baseline that is below the institutional LLN, permanently discontinue MEKINIST [see Dosage and Administration (2.4)].

5.6 Ocular Toxicities

Retinal Vein Occlusion

In the pooled safety population [see Adverse Reactions (6.1)] of MEKINIST monotherapy, the incidence of retinal vein occlusion (RVO) was 0.6%. In the pooled safety population [see Adverse Reactions (6.1)] of MEKINIST administered with dabrafenib, there were no cases of RVO. RVO may lead to macular edema, decreased visual function, neovascularization, and glaucoma.

Urgently (within 24 hours) perform ophthalmological evaluation for patient-reported loss of vision or other visual disturbances. Permanently discontinue MEKINIST in patients with documented RVO [see Dosage and Administration (2.4)].

Retinal Pigment Epithelial Detachment

Retinal pigment epithelial detachment (RPED) can occur with MEKINIST. Retinal detachments may be bilateral and multifocal, occurring in the central macular region of the retina or elsewhere in the retina. In melanoma and NSCLC trials, routine monitoring of patients to detect asymptomatic RPED was not conducted; therefore, the true incidence of this finding is unknown.

MEKINIST Administered with Dabrafenib (Pediatric): In the pooled safety population, RPED events occurred in < 1% of patients.

Perform ophthalmological evaluation periodically and at any time a patient reports visual disturbances. Withhold MEKINIST if RPED is diagnosed. If resolution of the RPED is documented on repeat ophthalmological evaluation within 3 weeks, resume MEKINIST at same or reduced dose. If no improvement after 3 weeks, resume MEKINIST at reduced dose or permanently discontinue MEKINIST [see Dosage and Administration (2.4)].

5.7 Interstitial Lung Disease/Pneumonitis

In the pooled safety population [see Adverse Reactions (6.1)] of MEKINIST monotherapy, interstitial lung disease or pneumonitis occurred in 2% of patients. In the pooled safety population [see Adverse Reactions (6.1)] of MEKINIST administered with dabrafenib, ILD or pneumonitis occurred in 1% of patients.

Withhold MEKINIST in patients presenting with new or progressive pulmonary symptoms and findings, including cough, dyspnea, hypoxia, pleural effusion, or infiltrates, pending clinical investigations. Permanently discontinue MEKINIST for patients diagnosed with treatment-related ILD or pneumonitis [see Dosage and Administration (2.4)].

5.8 Serious Febrile Reactions

Serious febrile reactions and fever of any severity accompanied by hypotension, rigors or chills, dehydration, or renal failure, can occur when MEKINIST is administered with dabrafenib.

MEKINIST Administered with Dabrafenib (Adult): In the pooled safety population [see Adverse Reactions (6.1)], fever occurred in 58% of patients. Serious febrile reactions and fever of any severity complicated by hypotension, rigors or chills, dehydration or renal failure occurred in 5% of patients. Fever was complicated by hypotension in 4%, dehydration in 3%, syncope in 2%, renal failure in 1%, and severe chills/rigors in < 1% of patients.

MEKINIST Administered with Dabrafenib (Pediatric): In the pooled safety population [see Adverse Reactions (6.1)], pyrexia occurred in 66% of patients.

Withhold MEKINIST when used as monotherapy, and both MEKINIST and dabrafenib when used in combination, if the patient’s temperature is ≥ 100.4°F. In case of recurrence, therapy can also be interrupted at the first symptom of pyrexia [see Adverse Reactions (6.1)]. Fever may be complicated by hypotension, rigors or chills, dehydration, or renal failure. Evaluate for signs and symptoms of infection and monitor serum creatinine and other evidence of renal function during and following severe pyrexia. If appropriate, MEKINIST, or both MEKINIST and dabrafenib when used in combination, may be restarted if the patient has recovered from the febrile reaction for at least 24 hours, either at same or lower dose [see Dosage and Administration (2.4)]. Administer antipyretics as secondary prophylaxis when resuming MEKINIST if patient had a prior episode of severe febrile reaction or fever associated with complications. Administer corticosteroids (e.g., prednisone 10 mg daily) for at least 5 days for second or subsequent pyrexia if temperature does not return to baseline within 3 days of onset of pyrexia, or for pyrexia associated with complications, such as dehydration, hypotension, renal failure, or severe chills/rigors, and there is no evidence of active infection.

5.9 Serious Skin Toxicities

Severe cutaneous adverse reactions (SCARs), including Stevens-Johnson syndrome (SJS) and drug reaction with eosinophilia and systemic symptoms (DRESS), which can be life-threatening or fatal, have been reported during treatment with MEKINIST administered with dabrafenib [see Adverse Reactions (6.2)].

MEKINIST Administered with Dabrafenib (Adult): In the pooled safety population [see Adverse Reactions (6.1)], other serious skin toxicity occurred in < 1% of patients.

MEKINIST Administered with Dabrafenib (Pediatric): In the pooled safety population, serious adverse events of skin and subcutaneous tissue disorders occurred in 1.8% of patients.

Monitor for new or worsening serious skin reactions. Permanently discontinue MEKINIST for SCARs [see Dosage and Administration (2.4)]. For other skin toxicities, withhold MEKINIST for intolerable or severe skin toxicity. Resume MEKINIST at a lower dose in patients with improvement or recovery from skin toxicity within 3 weeks. Permanently discontinue MEKINIST if skin toxicity has not improved in 3 weeks [see Dosage and Administration (2.4)].

5.10 Hyperglycemia

MEKINIST Administered with Dabrafenib (Adult): In the pooled safety population [see Adverse Reactions (6.1)], 15% of patients with a history of diabetes who had received MEKINIST with dabrafenib required more intensive hypoglycemic therapy. Grade 3 and Grade 4 hyperglycemia occurred in 2% of patients.

MEKINIST Administered with Dabrafenib (Pediatric): In the pooled safety population, Grade 3 and Grade 4 hyperglycemia events occurred in < 1% of patients.

Monitor serum glucose levels upon initiation and as clinically appropriate when MEKINIST is administered with dabrafenib in patients with preexisting diabetes or hyperglycemia. Initiate or optimize anti-hyperglycemic medications as clinically indicated.

5.11 Risks Associated with Combination Treatment

MEKINIST is indicated for use in combination with dabrafenib. Review the prescribing information for dabrafenib for information on the serious risks of dabrafenib prior to initiation of MEKINIST with dabrafenib.

5.12 Hemophagocytic Lymphohistiocytosis

Hemophagocytic lymphohistiocytosis (HLH) has been observed in the post-marketing setting when MEKINIST was administered with dabrafenib. If HLH is suspected, interrupt treatment. If HLH is confirmed, discontinue treatment and initiate appropriate management of HLH.

5.13 Embryo-Fetal Toxicity

Based on findings from animal studies and its mechanism of action, MEKINIST can cause fetal harm when administered to a pregnant woman. Trametinib was embryotoxic and abortifacient in rabbits at doses greater than or equal to those resulting in exposures approximately 0.3 times the human exposure at the recommended adult clinical dose. Advise pregnant women of the potential risk to a fetus. Advise female patients of reproductive potential to use effective contraception during treatment with MEKINIST and for 4 months after treatment [see Use in Specific Populations (8.1, 8.3)].

6 ADVERSE REACTIONS

The following clinically significant adverse reactions are described elsewhere in the labeling:

- New Primary Malignancies [see Warnings and Precautions (5.1)]
- Hemorrhage [see Warnings and Precautions (5.2)]
- Colitis and Gastrointestinal Perforation [see Warnings and Precautions (5.3)]
- Venous Thromboembolic Events [see Warnings and Precautions (5.4)]
- Cardiomyopathy [see Warnings and Precautions (5.5)]
- Ocular Toxicities [see Warnings and Precautions (5.6)]
- Interstitial Lung Disease/Pneumonitis [see Warnings and Precautions (5.7)]
- Serious Febrile Reactions [see Warnings and Precautions (5.8)]
- Serious Skin Toxicities [see Warnings and Precautions (5.9)]
- Hyperglycemia [see Warnings and Precautions (5.10)]
- Hemophagocytic Lymphohistiocytosis [see Warnings and Precautions (5.12)]

There are additional adverse reactions associated with dabrafenib. Refer to the dabrafenib prescribing information for additional information.

6.1 Clinical Trials Experience

Because clinical trials are conducted under widely varying conditions, adverse reaction rates observed in the clinical trials of a drug cannot be directly compared to rates in the clinical trials of another drug and may not reflect the rates observed in practice.

Adult Safety Pools

The pooled safety population described in the WARNINGS AND PRECAUTIONS reflects exposure to MEKINIST 2 mg orally, once daily as a single agent in 329 patients with various solid tumors enrolled in METRIC, MEK113583, and MEK111054. Among these 329 patients who received MEKINIST as a single agent, 33% were exposed for 6 months or longer and 9% were exposed for greater than one year.

The pooled safety population described in the WARNINGS AND PRECAUTIONS reflects exposure to MEKINIST 2 mg orally, once daily, administered in combination with dabrafenib 150 mg orally, twice daily, in 1087 patients enrolled in COMBI-d, COMBI-v, COMBI-AD, and BRF113928 with unresectable or metastatic melanoma, adjuvant melanoma, or NSCLC. Among these 1087 patients who received MEKINIST administered with dabrafenib, 70% were exposed for 6 months or longer and 21% were exposed for greater than one year.

Pediatric Safety Pool

The pediatric pooled safety population described in the WARNINGS AND PRECAUTIONS reflects exposure to weight-based MEKINIST orally, once daily administered in combination with dabrafenib in 166 pediatric patients across two trials: a multi-center, open-label, multi-cohort study in pediatric patients with BRAF V600E mutation-positive glioma requiring systemic therapy (Study G2201; n = 123) and a multi-center, open-label, multi-cohort study in pediatric patients with refractory or recurrent solid tumors with MAPK pathway activation (Study X2101; n = 43) [see Clinical Studies (14.6, 14.7)]. Among 166 patients who received MEKINIST administered with dabrafenib, 85% were exposed for 6 months and 69% were exposed for greater than one year. The most common (> 20%) adverse reactions were pyrexia (66%), rash (54%), headache (40%), vomiting (38%), musculoskeletal pain (36%), fatigue (31%), dry skin (31%), diarrhea (30%), nausea (26%), epistaxis and other bleeding events (25%), abdominal pain (24%), and dermatitis acneiform (23%). The most common (> 2%) Grade 3 or 4 laboratory abnormalities were decreased neutrophil count (20%), increased alanine aminotransferase (3.1%), and increased aspartate aminotransferase (3.1%).

Unresectable or Metastatic BRAF V600E or V600K Mutation-Positive Melanoma

MEKINIST as a Single Agent

The safety of MEKINIST was evaluated in the METRIC study, a randomized, open-label trial of patients with BRAF V600E or V600K mutation-positive unresectable or metastatic melanoma who received MEKINIST (N = 211) 2 mg orally once daily or chemotherapy (N = 99) (either dacarbazine 1000 mg/m^2 every 3 weeks or paclitaxel 175 mg/m^2 every 3 weeks) [see Clinical Studies (14.1)]. Patients with abnormal LVEF, history of acute coronary syndrome within 6 months, or current evidence of Class II or greater congestive heart failure (New York Heart Association) were excluded. The median duration of treatment with MEKINIST was 4.3 months.

In this study, 9% of patients who received MEKINIST experienced adverse reactions resulting in permanent discontinuation of trial medication. The most frequent adverse reactions resulting in permanent discontinuation of MEKINIST were decreased LVEF, pneumonitis, renal failure, diarrhea, and rash. Adverse reactions led to dose reductions in 27% of patients treated with MEKINIST. Rash and decreased LVEF were the most frequent reasons cited for dose reductions of MEKINIST. Table 6 and Table 7 present adverse reactions and laboratory abnormalities, respectively, of MEKINIST as a single agent in the METRIC study.

Table 6. Select Adverse Reactions Occurring in ≥ 10% of Patients Who Received MEKINIST and at a Higher Incidence (≥ 5%) Than in the Chemotherapy Arm or ≥ 2% (Grades 3 or 4) Adverse Reactions in the METRIC Study
Adverse Reactions | MEKINIST |  | Chemotherapy
 | N = 211 |  | N = 99
 | All Gradesa (%) | Grades 3 and 4 b (%) | All Gradesa (%) | Grades 3 and 4 b (%)
Skin and subcutaneous tissue
Rash | 57 | 8 | 10 | 0
Acneiform dermatitis | 19 | < 1 | 1 | 0
Dry skin | 11 | 0 | 0 | 0
Pruritus | 10 | 2 | 1 | 0
Paronychia | 10 | 0 | 1 | 0
Gastrointestinal
Diarrhea | 43 | 0 | 16 | 2
Stomatitisc | 15 | 2 | 2 | 0
Abdominal paind | 13 | 1 | 5 | 1
Vascular
Lymphedemae | 32 | 1 | 4 | 0
Hypertension | 15 | 12 | 7 | 3
Hemorrhagef | 13 | < 1 | 0 | 0
aNCI CTCAE version 4.0.
bGrade 4 adverse reactions limited to rash (n = 1) in trametinib arm and diarrhea (n = 1) in chemotherapy arm.
cIncludes stomatitis, aphthous stomatitis, mouth ulceration, and mucosal inflammation.
dIncludes abdominal pain, lower abdominal pain, upper abdominal pain, and abdominal tenderness.
eIncludes lymphedema, edema, and peripheral edema.
fIncludes epistaxis, gingival bleeding, hematochezia, rectal hemorrhage, melena, vaginal hemorrhage, hemorrhoidal hemorrhage, hematuria, and conjunctival hemorrhage.

Table 7. Laboratory Abnormalities Occurring at a Higher Incidence in Patients Who Received MEKINIST in the METRIC Study [Between-Arm Difference of ≥ 5% (All Grades) or ≥ 2% (Grades 3 or 4)a]
Laboratory Abnormality | MEKINIST |  | Chemotherapy
 | N = 211 |  | N = 99
 | All Grades (%) | Grades 3 and 4 (%) | All Grades (%) | Grades 3 and 4 (%)
Increased AST | 60 | 2 | 16 | 1
Hypoalbuminemia | 42 | 2 | 23 | 1
Increased ALT | 39 | 3 | 20 | 3
Anemia | 38 | 2 | 26 | 3
Increased alkaline phosphatase | 24 | 2 | 18 | 3
Abbreviations: ALT, alanine aminotransferase; AST, aspartate aminotransferase.
aOnly Grade 3 adverse reactions were reported in either treatment arm.

Other clinically important adverse reactions for MEKINIST in a pool of MEKINIST monotherapy clinical studies observed in less than 10% of patients who received MEKINIST were:

Cardiac: Bradycardia, atrioventricular block, bundle branch block

Gastrointestinal: Dry mouth

Infections and Infestations: Folliculitis, rash pustular, cellulitis

Musculoskeletal and Connective Tissue: Rhabdomyolysis

Nervous System: Dizziness, dysgeusia, peripheral neuropathy

Ocular: Blurred vision, dry eye

MEKINIST with Dabrafenib

The safety of MEKINIST when administered with dabrafenib was evaluated in 559 patients with previously untreated, unresectable or metastatic, BRAF V600 mutation-positive melanoma who received MEKINIST in two trials, the COMBI-d study (n = 209), a multi-center, double-blind, randomized (1:1), active-controlled trial and the COMBI-v study (n = 350), a multi-center, open-label, randomized (1:1), active-controlled trial. In both trials, patients received MEKINIST 2 mg orally once daily and dabrafenib 150 mg orally twice daily until disease progression or unacceptable toxicity. Both trials excluded patients with abnormal LVEF, history of acute coronary syndrome within 6 months, history of Class II or greater congestive heart failure (New York Heart Association), history of RVO or RPED, QTcB interval ≥ 480 msec, uncontrolled hypertension, uncontrolled arrhythmias, active brain metastases, or known history of glucose-6-phosphate dehydrogenase deficiency [see Clinical Studies (14.1)].

Among these 559 patients, 197 (35%) were exposed to MEKINIST for > 6 months to 12 months while 185 (33%) were exposed to MEKINIST for > 1 year. The median age was 55 years (range: 18 to 91), 57% were male, and 98% were White, 72% had baseline ECOG performance status of 0 and 28% had ECOG performance status of 1, 64% had M1c disease, 35% had elevated lactate dehydrogenase (LDH) at baseline, and 0.5% had a history of brain metastases.

The most common adverse reactions (≥ 20%) for MEKINIST in patients who received MEKINIST plus dabrafenib in the COMBI-d and COMBI-v studies were: pyrexia, nausea, rash, chills, diarrhea, vomiting, hypertension, and peripheral edema.

The demographics and baseline tumor characteristics of patients enrolled in the COMBI-d study are summarized in Clinical Studies [see Clinical Studies (14.1)]. Patients who received MEKINIST plus dabrafenib had a median duration of exposure of 11 months (range: 3 days to 30 months) to MEKINIST. Among the 209 patients who received MEKINIST plus dabrafenib, 26% were exposed to MEKINIST for > 6 months to 12 months while 46% were exposed to MEKINIST for > 1 year.

In the COMBI-d study, adverse reactions leading to discontinuation of MEKINIST occurred in 11% of patients who received MEKINIST plus dabrafenib; the most frequent were pyrexia (1.4%) and decreased ejection fraction (1.4%). Adverse reactions leading to dose reductions of MEKINIST occurred in 18% of patients who received MEKINIST plus dabrafenib; the most frequent were pyrexia (2.9%), neutropenia (1.9%), decreased ejection fraction (1.9%), and rash (1.9%). Adverse reactions leading to dose interruptions of MEKINIST occurred in 46% of patients who received MEKINIST plus dabrafenib; the most frequent were pyrexia (18%), chills (7%), vomiting (6%), and decreased ejection fraction (4.8%).

Table 8 and Table 9 present selected adverse reactions and laboratory abnormalities, respectively, of MEKINIST observed in the COMBI-d study.

Table 8. Adverse Reactions Occurring in ≥ 10% (All Grades) of Patients Who Received MEKINIST with Dabrafenib and at a Higher Incidence* Than in Patients Who Received Single-Agent Dabrafenib in COMBI-da
Adverse Reactions | Pooled MEKINIST plus Dabrafenib N = 559 |  | COMBI-d Study
 |  |  | MEKINIST plus Dabrafenib N = 209 |  | Dabrafenib N = 211
 | All Grades (%) | Grades 3 and 4 (%) | All Grades (%) | Grades 3 and 4 (%) | All Grades (%) | Grades 3 and 4 (%)
General
Pyrexia | 54 | 5 | 57 | 7 | 33 | 1.9
Chills | 31 | 0.5 | 31 | 0 | 17 | 0.5
Peripheral edemab | 21 | 0.7 | 25 | 1.4 | 11 | 0.5
Gastrointestinal
Nausea | 35 | 0.4 | 34 | 0.5 | 27 | 1.4
Diarrhea | 31 | 1.3 | 30 | 1.4 | 16 | 0.9
Vomiting | 27 | 1.1 | 25 | 1.0 | 14 | 0.5
Abdominal painc | 18 | 0.9 | 26 | 1.0 | 14 | 2.4
Skin and subcutaneous tissue
Rashd | 32 | 1.1 | 42 | 0 | 27 | 1.4
Vascular
Hypertension | 26 | 11 | 25 | 6 | 16 | 6
Hemorrhagee | 18 | 2.0 | 19 | 1.9 | 15 | 1.9
Nervous system
Dizziness | 11 | 0.2 | 14 | 0 | 7 | 0
* ≥ 5% for All Grades or ≥ 2% for Grades 3–4 incidence in patients who received MEKINIST with dabrafenib compared with patients who received dabrafenib as a single agent.
aNCI CTCAE version 4.0.
bIncludes peripheral edema, edema, lymphedema, localized edema, and generalized edema.
cIncludes abdominal pain, upper abdominal pain, lower abdominal pain, and abdominal discomfort.
dIncludes rash, generalized rash, pruritic rash, erythematous rash, papular rash, vesicular rash, macular rash, maculo-papular rash, and follicular rash.
eMost common events (≥ 1%) include epistaxis, hematochezia, decreased hemoglobin, purpura, and rectal hemorrhage. Grade 4 events were limited to hepatic hematoma and duodenal ulcer hemorrhage (each n = 1 in the pooled combination arm).

Other clinically important adverse reactions for MEKINIST across the COMBI-d and COMBI-v studies (N = 559) observed in less than 10% of patients who received MEKINIST in combination with dabrafenib were:

Cardiac: Bradycardia, atrioventricular block, bundle branch block

Immune System: Sarcoidosis

Musculoskeletal and Connective Tissue: Rhabdomyolysis

Nervous System: Peripheral neuropathy, Guillain-Barré syndrome

Skin and Subcutaneous Tissue: Photosensitivity

Table 9. Laboratory Abnormalities Worsening from Baseline Occurring at ≥ 10% (All Grades) of Patients Who Received MEKINIST with Dabrafenib and at a Higher Incidence* Than in Patients Who Received Single-Agent Dabrafenib in COMBI-d
Laboratory Abnormality | Pooled MEKINIST plus Dabrafenib N = 559a |  | COMBI-d Study
 |  |  | MEKINIST plus Dabrafenib N = 209b |  | Dabrafenib N = 211b
 | All Grades (%) | Grades 3 and 4c (%) | All Grades (%) | Grades 3 and 4c (%) | All Grades (%) | Grades 3 and 4c (%)
Chemistry
Hyperglycemia | 60 | 4.7 | 65 | 6 | 57 | 4.3
Hypoalbuminemia | 48 | 1.1 | 53 | 1.4 | 27 | 0
Hyponatremia | 25 | 8 | 24 | 6 | 14 | 2.9
Hepatic
Increased AST | 59 | 4.1 | 60 | 4.3 | 21 | 1.0
Increased blood alkaline phosphatase | 49 | 2.7 | 50 | 1.0 | 25 | 0.5
Increased ALT | 48 | 4.5 | 44 | 3.8 | 28 | 1.0
Hematology
Neutropenia | 46 | 7 | 50 | 6 | 16 | 1.9
Anemia | 43 | 2.3 | 43 | 2.4 | 38 | 4.3
Lymphopenia | 32 | 8 | 38 | 9 | 28 | 7
Thrombocytopenia | 21 | 0.7 | 19 | 0.5 | 10 | 0.5
Abbreviations: ALT, alanine aminotransferase; AST, aspartate aminotransferase.
* ≥ 5% for All Grades or ≥ 2% for Grades 3–4 incidence in patients who received MEKINIST with dabrafenib compared with patients who received dabrafenib as a single agent.
aFor these laboratory tests, the denominator is 556.
bFor these laboratory tests, the denominator is 208 for the combination arm, 207-209 for the dabrafenib arm.
cGrade 4 adverse reactions limited to lymphopenia and hyperglycemia (each n = 4), increased ALT and increased AST (each n = 3), neutropenia (n = 2), and hyponatremia (n = 1) in the pooled combination arm; neutropenia, lymphopenia, increased ALT, increased AST, and hyperglycemia (each n = 1) in the COMBI-d study combination arm; neutropenia, thrombocytopenia, increased ALT, and increased AST (each n = 1) in the dabrafenib arm.

Adjuvant Treatment of BRAF V600E or V600K Mutation-Positive Melanoma

The safety of MEKINIST when administered with dabrafenib was evaluated in 435 patients with Stage III melanoma with BRAF V600E or V600K mutations following complete resection who received at least one dose of study therapy in the COMBI-AD study [see Clinical Studies (14.2)]. Patients received MEKINIST 2 mg orally once daily and dabrafenib 150 mg orally twice daily for 12 months. The trial excluded patients with abnormal LVEF; history of acute coronary syndromes, coronary angioplasty, or stenting within 6 months; Class II or greater congestive heart failure (New York Heart Association); QTc interval ≥ 480 msec; treatment refractory hypertension; uncontrolled arrhythmias; or history of RVO.

Patients who received MEKINIST in combination with dabrafenib had a median duration of exposure of 11 months (range: 0 to 12) to MEKINIST. Among the 435 patients who received MEKINIST in combination with dabrafenib, 72% were exposed to MEKINIST for > 6 months. The median age of patients who received MEKINIST in combination with dabrafenib was 50 years (range: 18 to 89), 56% were male, 99% were White, 92% had baseline ECOG performance status of 0, and 8% had baseline ECOG performance status of 1.

The most common adverse reactions (≥ 20%) in patients who received MEKINIST in combination with dabrafenib were: pyrexia, fatigue, nausea, headache, rash, chills, diarrhea, vomiting, arthralgia, and myalgia.

Adverse reactions resulting in discontinuation and dose interruptions of MEKINIST occurred in 24% and 54% of patients, respectively; the most frequent for each were pyrexia and chills. Adverse reactions leading to dose reductions of MEKINIST occurred in 23% of patients; the most frequent were pyrexia and decreased ejection fraction.

Table 10 summarizes the adverse reactions that occurred in at least 20% of the patients who received MEKINIST in combination with dabrafenib.

Table 10. Adverse Reactions Occurring in ≥ 20% of Patients in the COMBI-AD Studya
Adverse Reactions | MEKINIST plus Dabrafenib N = 435 |  | Placebo N = 432
 | All Grades (%) | Grades 3 and 4 (%) | All Grades (%) | Grades 3 and 4 (%)
General
Pyrexiab | 63 | 5 | 11 | < 1
Fatiguec | 59 | 5 | 37 | < 1
Chills | 37 | 1 | 4 | 0
Gastrointestinal
Nausea | 40 | < 1 | 20 | 0
Diarrhea | 33 | < 1 | 15 | < 1
Vomiting | 28 | < 1 | 10 | 0
Nervous system
Headached | 39 | 1 | 24 | 0
Skin and subcutaneous tissue
Rashe | 37 | < 1 | 16 | < 1
Musculoskeletal and connective tissue
Arthralgia | 28 | < 1 | 14 | 0
Myalgiaf | 20 | < 1 | 14 | 0
aNCI CTCAE version 4.0.
bIncludes pyrexia and hyperpyrexia.
cIncludes fatigue, asthenia, and malaise.
dIncludes headache and tension headache.
eIncludes rash, rash maculo-papular, rash macular, rash generalized, rash erythematous, rash papular, rash pruritic, nodular rash, rash vesicular, and rash pustular.
fIncludes myalgia, musculoskeletal pain, and musculoskeletal chest pain.

Other clinically important adverse reactions for MEKINIST in the COMBI-AD study observed in less than 20% of patients who received MEKINIST in combination with dabrafenib were: blurred vision (6%), decreased ejection fraction (5%), peripheral neuropathy (2.5%), rhabdomyolysis (< 1%), atrioventricular block (< 1%), Guillain-Barré syndrome (< 1%), and sarcoidosis (< 1%).

The laboratory abnormalities are summarized in Table 11.

Table 11. Laboratory Abnormalities Worsening from Baseline Occurring in ≥ 20% of Patients in the COMBI-AD Study
Laboratory Abnormality | MEKINIST plus Dabrafeniba N = 435 |  | Placeboa N = 432
 | All Grades (%) | Grades 3 and 4 (%) | All Grades (%) | Grades 3 and 4 (%)
Chemistry
Hyperglycemia | 63 | 3 | 47 | 2
Hypophosphatemia | 42 | 7 | 10 | < 1
Hypoalbuminemia | 25 | < 1 | < 1 | 0
Hepatic
Increased AST | 57 | 6 | 11 | < 1
Increased ALT | 48 | 5 | 18 | < 1
Increased blood alkaline phosphatase | 38 | 1 | 6 | < 1
Hematology
Neutropenia | 47 | 6 | 12 | < 1
Lymphopenia | 26 | 5 | 6 | < 1
Anemia | 25 | < 1 | 6 | < 1
Abbreviations: ALT, alanine aminotransferase; AST, aspartate aminotransferase.
aThe incidence is based on the number of patients who had both a baseline and at least one on-study laboratory measurement:
MEKINIST plus Dabrafenib (range: 429 to 431) and Placebo arm (range: 426 to 428).

Trial COMBI-APlus (Pyrexia Management Study)

COMBI-APlus evaluated the impact of pyrexia-related outcomes of a revised pyrexia management algorithm in patients who received dabrafenib administered with trametinib in the adjuvant treatment of BRAF V600 mutation-positive melanoma after complete resection. The pyrexia management algorithm interrupted both dabrafenib and trametinib when patient’s temperature is ≥ 100.4°F.

Grade 3-4 pyrexia occurred in 4.3% of patients, hospitalizations due to pyrexia occurred in 5.1% of patients, pyrexia with complications (dehydration, hypotension, renal dysfunction, syncope, severe chills) occurred in 2.2% of patients, and treatment discontinuation due to pyrexia occurred in 2.5% of patients.

Metastatic, BRAF V600E Mutation-Positive Non-Small Cell Lung Cancer

The safety of MEKINIST when administered with dabrafenib was evaluated in 93 patients with previously untreated (n = 36) and previously treated (n = 57) metastatic BRAF V600E mutation-positive NSCLC in a multi-center, multi-cohort, non-randomized, open-label trial (Study BRF113928). Patients received MEKINIST 2 mg orally once daily and dabrafenib 150 mg orally twice daily until disease progression or unacceptable toxicity. The trial excluded patients with abnormal LVEF, history of acute coronary syndrome within 6 months, history of Class II or greater congestive heart failure (New York Heart Association), QTc interval ≥ 480 msec, treatment refractory hypertension, uncontrolled arrhythmias, active brain metastases, history of ILD or pneumonitis, or history or current RVO [see Clinical Studies (14.3)].

Among these 93 patients, 53 (57%) were exposed to MEKINIST and dabrafenib for > 6 months and 27 (29%) were exposed to MEKINIST and dabrafenib for ≥ 1 year. The median age was 65 years (range: 41 to 91), 46% were male, 85% were White; 32% had baseline ECOG performance status of 0 and 61% had ECOG performance status of 1; 98% had non-squamous histology; and 12% were current smokers, 60% were former smokers, and 28% had never smoked.

The most common adverse reactions (≥ 20%) in these 93 patients were: pyrexia, fatigue, nausea, vomiting, diarrhea, dry skin, decreased appetite, edema, rash, chills, hemorrhage, cough, and dyspnea.

Adverse reactions leading to discontinuation of MEKINIST occurred in 19% of patients; the most frequent were pyrexia (2.2%), decreased ejection fraction (2.2%), and respiratory distress (2.2%). Adverse reactions leading to dose reductions of MEKINIST occurred in 30% of patients; the most frequent were pyrexia (5%), nausea (4.3%), vomiting (4.3%), diarrhea (3.2%), and neutropenia (3.2%). Adverse reactions leading to dose interruptions of MEKINIST occurred in 57% of patients; the most frequent were pyrexia (16%), vomiting (10%), neutropenia (8%), nausea (5%), and decreased ejection fraction (5%).

Table 12 and Table 13 present adverse reactions and laboratory abnormalities, respectively, of MEKINIST in combination with dabrafenib in Study BRF113928.

Table 12. Adverse Reactions Occurring in ≥ 20% (All Grades) of Patients Treated with MEKINIST plus Dabrafenib in Study BRF113928a
Adverse Reactions | MEKINIST plus Dabrafenib N = 93
 | All Grades (%) | Grades 3 and 4 (%)
General
Pyrexia | 55 | 5
Fatigueb | 51 | 5
Edemac | 28 | 0
Chills | 23 | 1.1
Gastrointestinal
Nausea | 45 | 0
Vomiting | 33 | 3.2
Diarrhea | 32 | 2.2
Decreased appetite | 29 | 0
Skin and subcutaneous tissue
Dry skin | 31 | 1.1
Rashd | 28 | 3.2
Vascular
Hemorrhagee | 23 | 3.2
Respiratory system
Cough | 22 | 0
Dyspnea | 20 | 5
aNCI CTCAE version 4.0.
bIncludes fatigue, malaise, and asthenia.
cIncludes peripheral edema, edema, and generalized edema.
dIncludes rash, rash generalized, rash papular, rash macular, rash maculo-papular, and rash pustular.
eIncludes hemoptysis, hematoma, epistaxis, purpura, hematuria, subarachnoid hemorrhage, gastric hemorrhage, urinary bladder hemorrhage, contusion, hematochezia, injection site hemorrhage, pulmonary hemorrhage, and retroperitoneal hemorrhage.

Other clinically important adverse reactions for MEKINIST in Study BRF113928 observed in less than 20% of patients who received MEKINIST administered with dabrafenib were:

Cardiac: Atrioventricular block

Nervous System: Peripheral neuropathy

Table 13. Treatment-Emergent Laboratory Abnormalities Occurring in ≥ 20% (All Grades) of Patients Who Received MEKINIST plus Dabrafenib in Study BRF113928
Laboratory Abnormality | MEKINIST plus Dabrafenib N = 93
 | All Grades (%) | Grades 3 and 4 (%)
Chemistrya
Hyperglycemia | 71 | 9
Hyponatremia | 57 | 17
Hypophosphatemia | 36 | 7
Increased creatinine | 21 | 1.1
Hepatica
Increased blood alkaline phosphatase | 64 | 0
Increased AST | 61 | 4.4
Increased ALT | 32 | 6
Hematologyb
Leukopenia | 48 | 8
Anemia | 46 | 10
Neutropenia | 44 | 8
Lymphopenia | 42 | 14
Abbreviations: ALT, alanine aminotransferase; AST, aspartate aminotransferase.
aFor these laboratory tests, the denominator is 90.
bFor these laboratory tests, the denominator is 91.

Advanced BRAF V600E Mutation-Positive Tumors

Study BRF117019

The safety of MEKINIST when administered with dabrafenib was evaluated in a multi-cohort, multi-center, non-randomized, open-label study in adult patients with cancers with the BRAF V600E mutation (Study BRF117019). A total of 206 patients were enrolled in the trial, 36 of whom were enrolled in the ATC cohort, 105 were enrolled in specific solid tumor cohorts, and 65 in other malignancies [see Clinical Studies (14.4, 14.6)]. Patients received MEKINIST 2 mg orally once daily and dabrafenib 150 mg orally twice daily until disease progression or unacceptable toxicity.

Among these 206 patients, 101 (49%) were exposed to MEKINIST for ≥ 1 year and 103 (50%) were exposed to dabrafenib for ≥ 1 year. The median age was 60 years (range: 18 to 89); 56% were male; 79% were White; and 34% had baseline ECOG performance status of 0 and 60% had ECOG performance status of 1.

Serious adverse reactions occurred in 45% of patients who received MEKINIST in combination with dabrafenib. Serious adverse reactions in > 5% of patients included pyrexia (11%) and pneumonia (6%). Fatal adverse reactions occurred in 3.9% of patients who received MEKINIST in combination with dabrafenib. Fatal adverse reactions that occurred in > 1% of patients included sepsis (1.9%).

Permanent treatment discontinuation due to an adverse reaction occurred in 13% of patients. Adverse reactions which resulted in permanent treatment discontinuation in > 1% of patients included nausea (1.5%).

Dosage interruptions due to an adverse reaction occurred in 55% of patients. Adverse reactions which required dosage interruption in > 5% of patients included pyrexia (22%), chills (9%), fatigue (6%), neutropenia (6%), and nausea (5%).

Dose reductions due to an adverse reaction occurred in 44% of patients. Adverse reactions which required dose reductions in > 5% of patients included pyrexia (18%), chills (8%), and fatigue (6%).

The most common (≥ 20%) adverse reactions, including laboratory abnormalities, are listed in Table 14 and Table 15.

Table 14 summarizes the adverse reactions in Study BRF117019.

Table 14. Adverse Reactions (≥ 20%) in Adult Patients Treated with MEKINIST Plus Dabrafenib in Study BRF117019
Adverse Reactions | MEKINIST plus Dabrafeniba (N = 206)
 | All Grades (%) | Grade 3 or 4 (%)
General
Pyrexia | 55 | 4.95
Fatigueb | 50 | 5
Chills | 30 | 0.5
Peripheral edemac | 22 | 0
Gastrointestinal
Nausea | 40 | 1.5
Constipation | 27 | 0
Vomiting | 27 | 1.5
Diarrhea | 26 | 2.93
Skin and subcutaneous tissue
Rashd | 40 | 2.4
Nervous system
Headache | 30 | 1.5
Vascular
Hemorrhagee | 29 | 4.4
Respiratory system
Coughf | 29 | 0
Musculoskeletal and connective tissue
Myalgiag | 24 | 0.5
Arthralgia | 23 | 0.5
aNCI CTCAE version 4.0.
bIncludes fatigue, asthenia, and malaise.
cIncludes peripheral edema and peripheral swelling.
dIncludes rash, rash maculo-papular, rash erythematous, rash pustular, and rash papular.
eIncludes epistaxis, hematuria, contusion, hematoma, hemoptysis, conjunctival hemorrhage, hematochezia, rectal hemorrhage, hemorrhoidal hemorrhage, melaena, purpura, eye contusion, eye hemorrhage, gastric hemorrhage, gingival bleeding, hematemesis, hemorrhage intracranial, hemorrhagic stroke, hemothorax, increased tendency to bruise, large intestinal hemorrhage, mouth hemorrhage, petechiae, pharyngeal hemorrhage, prothrombin time prolonged, pulmonary hematoma, retinal hemorrhage, vaginal hemorrhage, and vitreous hemorrhage.
fIncludes cough and productive cough.
gIncludes myalgia, musculoskeletal chest pain, and musculoskeletal pain.

Clinically relevant adverse reactions for MEKINIST in Study BRF117019 observed in less than 20% of patients who received MEKINIST in combination with dabrafenib were: peripheral neuropathy (9%), decreased ejection fraction (8%), atrioventricular block (2.9%), uveitis (1.9%), hypersensitivity (1.9%) and Guillain-Barré syndrome (< 1%).

Table 15 summarizes the laboratory abnormalities in Study BRF117019.

Table 15. Select Laboratory Abnormalities (≥ 20%) That Worsened from Baseline in Adult Patients Treated with MEKINIST Plus Dabrafenib in Study BRF117019
Laboratory Abnormality | MEKINIST plus Dabrafeniba
 | All Grades (%) | Grade 3 or 4 (%)
Chemistry
Hyperglycemia | 61 | 8
Decreased sodium | 35 | 10
Decreased magnesium | 24 | 0
Increased creatinine | 21 | 1.5
Hepatic
Increased alkaline phosphatase | 51 | 5
Increased AST | 51 | 4.6
Increased ALT | 39 | 3
Hematology
Decreased hemoglobin | 44 | 9
Abbreviations: ALT, alanine aminotransferase; AST, aspartate aminotransferase.
aThe denominator used to calculate the rate varied from 199 to 202 based on the number of patients with a baseline value and at least one post-treatment value.

BRAF V600E Mutation-Positive Solid Tumors in Pediatric Patients

Study CTMT212X2101 (X2101)

The safety of MEKINIST when administered with dabrafenib was evaluated in Study X2101, a multi-center, open-label, multi-cohort study in pediatric patients (n = 48) with refractory or recurrent solid tumors activation [see Clinical Studies (14.6)]. The median duration of exposure to MEKINIST in Parts C (dose escalation) and D (cohort expansion) was 20.8 and 24.4 months, respectively. The median duration of exposure to dabrafenib in Parts C and D was 20.8 and 24.9 months, respectively. The median age of pediatric patients who received MEKINIST with dabrafenib was 9 years (range: 1 to 17).

Serious adverse reactions occurred in 46% of patients who received MEKINIST in combination with dabrafenib. Serious adverse reactions in > 5% of patients included pyrexia (25%) and decreased ejection fraction (6%). Permanent treatment discontinuation due to an adverse reaction occurred in 21% of patients. Adverse reactions which resulted in permanent treatment discontinuation in > 3% of patients included increased ALT (6%), increased AST (4.2%) and decreased ejection fraction (4.2%). Dosage interruptions due to an adverse reaction occurred in 73% of patients. Adverse reactions which required dosage interruption in > 5% of patients included pyrexia (56%), vomiting (19%), neutropenia (13%), rash (13%), decreased ejection fraction (6%), and uveitis (6%). Dose reductions due to an adverse reaction occurred in 25% of patients. Adverse reactions which required dose reductions in > 5% of patients included pyrexia (13%).

The most common (≥ 20%) adverse reactions, including laboratory abnormalities, are listed in Table 16 and Table 17.

Table 16 summarizes the adverse reactions in Study X2101.

Table 16. Adverse Reactions (≥ 20%) in Pediatric Patients Treated with MEKINIST Plus Dabrafenib in Study X2101
Adverse Reactions | MEKINIST plus Dabrafeniba (N = 48)
 | All Grades (%) | Grade 3 or 4 (%)
General
Pyrexia | 75 | 17
Fatigueb | 48 | 0
Skin and subcutaneous tissue
Rashc | 73 | 2.1
Dry skin | 48 | 0
Dermatitis acneiformd | 40 | 0
Gastrointestinal
Vomiting | 52 | 4.2
Diarrhea | 42 | 2.1
Abdominal paine | 33 | 4.2
Nausea | 33 | 2.1
Constipation | 23 | 0
Respiratory system
Cough | 44 | 0
Nervous system
Headache | 35 | 0
Vascular
Hemorrhagef | 33 | 0
Infections and infestations
Paronychia | 23 | 0
aNCI CTCAE version 4.0.
bIncludes fatigue, asthenia, and malaise.
cIncludes rash, rash maculo-papular, rash erythematous, rash papular, rash pustular, and rash macular.
dIncludes dermatitis acneiform and acne.
eIncludes abdominal pain and abdominal pain upper.
fIncludes epistaxis, hematuria, contusion, hematoma, petechiae, rectal hemorrhage, and red blood cell count decreased.

Clinically relevant adverse reactions for MEKINIST in Study X2101 observed in less than 20% of patients (N=48) who received MEKINIST in combination with dabrafenib were: atrioventricular block (2.1%).

Table 17 summarizes the laboratory abnormalities in Study X2101.

Table 17. Select Laboratory Abnormalities (≥ 20%) That Worsened from Baseline in Pediatric Patients Treated with MEKINIST Plus Dabrafenib in Study X2101
Laboratory Abnormality | MEKINIST plus Dabrafeniba
 | All Grades (%) | Grade 3 or 4 (%)
Chemistry
Hyperglycemia | 65 | 2.2
Hypoalbuminemia | 48 | 2.1
Hypocalcemia | 40 | 2.1
Decreased phosphate | 38 | 0
Decreased magnesium | 33 | 2.1
Hypernatremia | 27 | 0
Hypokalemia | 21 | 2.1
Hepatic
Increased AST | 55 | 4.2
Increased ALT | 40 | 6
Increased alkaline phosphatase | 28 | 6
Increased total bilirubin | 21 | 2.1
Hematology
Decreased hemoglobin | 60 | 6
Decreased neutrophils | 49 | 28
Abbreviations: ALT, alanine aminotransferase; AST, aspartate aminotransferase.
aThe denominator used to calculate the rate varied from 39 to 48 based on the number of patients with a baseline value and at least one post-treatment value.

BRAF V600E Mutation-Positive Low-Grade Glioma in Pediatric Patients

Study CDRB436G2201 (G2201)

The safety of MEKINIST in combination with dabrafenib was evaluated in pediatric patients 1 to < 18 years of age in Study G2201. Patients with low-grade glioma (LGG) who required first systemic therapy were randomized (2:1) to MEKINIST plus dabrafenib (n = 73) or carboplatin plus vincristine (n = 33). Nine patients crossed over from the carboplatin plus vincristine arm to the MEKINIST and dabrafenib arm. Pediatric patients received weight-based MEKINIST orally once daily administered in combination with dabrafenib until disease progression or intolerable toxicity. Patients in the control arm received carboplatin and vincristine at doses of 175 mg/m^2 and 1.5 mg/m^2, respectively in 10-week induction course followed by eight 6-week cycles of maintenance therapy or until disease progression or intolerable toxicity. Among patients with low-grade glioma who were randomized to MEKINIST plus dabrafenib (n = 73), 95% were exposed for 6 months or longer and 71% were exposed for greater than one year.

The median age of these patients was 10 years (range: 1 to 17); 60% female; 75% White, 7% Asian, 2.7% Black or African American, 4% other race, and 11% where race was unknown or not reported.

Serious adverse reactions occurred in 40% of these patients. Serious adverse reactions in > 3% of patients included pyrexia (14%) and vomiting (4%).

Permanent discontinuation of MEKINIST due to an adverse reaction occurred in 4% of patients. Adverse reactions which resulted in permanent discontinuation of MEKINIST included chills, fatigue, pyrexia, weight increased, and headache.

Dosage interruptions of MEKINIST due to an adverse reaction occurred in 70% of patients. Adverse reactions which required a dosage interruption in > 5% of patients included pyrexia (52%).

Dose reductions of MEKINIST due to an adverse reaction occurred in 12% of patients. Adverse reactions which required dose reductions in > 2% of patients included weight increased (2.7%).

The most common (≥ 15%) adverse reactions were pyrexia (68%), rash (51%), headache (47%), vomiting (34%), musculoskeletal pain (34%), fatigue (33%), diarrhea (29%), dry skin (26%), nausea (25%), hemorrhage (25%), abdominal pain (25%), dermatitis acneiform (22%), dizziness (15%), upper respiratory tract infection (15%), and weight increased (15%).

The most common (≥ 20%) laboratory abnormalities that worsened from baseline were leukopenia (59%), increased alkaline phosphatase (55%), anemia (46%), decreased neutrophils (44%), increased AST (37%), decreased magnesium (34%), increased magnesium (32%), decreased platelets (30%), increased ALT (29%), and increased lymphocytes (24%).

Table 18 summarizes the adverse reactions in Study G2201.

Table 18. Adverse Reactions (≥ 15%) in Pediatric LGG Patients Who Received MEKINIST in Combination with Dabrafenib in Study G2201a
Adverse Reactions | MEKINIST plus Dabrafenib N = 73 |  | Carboplatin plus Vincristine N = 33
 | All Grades (%) | Grade ≥ 3 (%) | All Grades (%) | Grade ≥ 3 (%)
Gastrointestinal
Vomiting | 34 | 1 | 48 | 3
Diarrheab | 29 | 0 | 18 | 6
Nausea | 25 | 0 | 45 | 0
Abdominal painc | 25 | 0 | 24 | 0
Constipation | 12 | 0 | 36 | 0
Stomatitisd | 10 | 0 | 18 | 0
General
Pyrexiae | 68 | 8 | 18 | 3
Fatiguef | 33 | 0 | 39 | 0
Nervous system
Headacheg | 47 | 1 | 33 | 3
Dizzinessh | 15 | 0 | 9 | 3
Peripheral neuropathyi | 7 | 0 | 45 | 6
Vascular
Hemorrhagej | 25 | 0 | 12 | 0
Skin and subcutaneous tissue
Rashk | 51 | 2.7 | 18 | 3
Dry skin | 26 | 0 | 3 | 0
Dermatitis acneiforml | 22 | 0 | 0 | 0
Alopecia | 3 | 0 | 24 | 0
Musculoskeletal and connective tissue
Musculoskeletal painm | 34 | 0 | 30 | 0
Pain in jaw | 1.4 | 0 | 18 | 0
Metabolism and nutrition
Decreased appetite | 5 | 0 | 24 | 0
Respiratory, thoracic and mediastinal
Oropharyngeal pain | 11 | 0 | 18 | 0
Psychiatric
Anxiety | 1.4 | 0 | 15 | 3
Immune system
Hypersensitivity | 0 | 0 | 15 | 3
Infections and infestations
Upper respiratory tract infection | 15 | 0 | 6 | 0
Injury, poisoning and procedural complications
Infusion-related reaction | 0 | 0 | 15 | 3
Investigations
Weight increased | 15 | 7 | 0 | 0
aNCI CTCAE version 4.03.
bIncludes diarrhea, colitis, enterocolitis, and enteritis.
cIncludes abdominal pain and upper abdominal pain.
dIncludes stomatitis, cheilitis, mouth ulceration, aphthous ulcer, and glossitis.
eIncludes pyrexia and body temperature increased.
fIncludes fatigue and asthenia.
gIncludes headache and migraine with aura.
hIncludes dizziness and vertigo.
iIncludes peripheral neuropathy, peripheral motor neuropathy, peripheral sensorimotor neuropathy, paresthesia, neuralgia, hypoaesthesia, and peripheral sensory neuropathy.
jIncludes epistaxis, post-procedural hemorrhage, hematuria, upper gastrointestinal hemorrhage, and hemorrhage intracranial.
kIncludes rash, rash macular, rash maculo-papular, rash pustular, rash papular, rash erythematous, eczema, erythema multiforme, dermatitis, dermatitis exfoliative, skin exfoliation, palmar-plantar erythrodysaesthesia syndrome, and dermatitis bullous.
lIncludes dermatitis acneiform, acne, and acne pustular.
mIncludes back pain, myalgia, pain in extremity, arthralgia, bone pain, non-cardiac chest pain, neck pain, and musculoskeletal stiffness.

Table 19 summarizes the laboratory abnormalities in Study G2201.

Table 19. Select Laboratory Abnormalities (≥ 20%) That Worsened from Baseline in Pediatric LGG Patients Who Received MEKINIST in Combination with Dabrafenib in Study G2201a
Laboratory Abnormality | MEKINIST plus Dabrafenib N = 73 |  | Carboplatin plus Vincristine N = 33
 | All Grades (%) | Grade 3 or 4 (%) | All Grades (%) | Grade 3 or 4 (%)
Hepatic
Increased alkaline phosphatase | 55 | 0 | 13 | 0
Increased AST | 37 | 1.4 | 55 | 0
Increased ALT | 29 | 3 | 61 | 9
Chemistry
Decreased magnesium | 34 | 4.1 | 76 | 6
Increased magnesium | 32 | 0 | 24 | 3
Increased potassium | 15 | 4.2 | 21 | 6
Decreased calcium | 14 | 4.1 | 22 | 9
Decreased potassium | 8 | 1.4 | 70 | 0
Decreased phosphate | 7 | 2.7 | 33 | 3
Decreased sodium | 5 | 1.4 | 27 | 6
Increased serum fasting glucose | 0 | 0 | 44 | 0
Hematology
Decreased leukocytes | 59 | 0 | 91 | 18
Decreased hemoglobin | 46 | 0 | 94 | 36
Decreased neutrophils | 44 | 17 | 84 | 75
Decreased platelets | 30 | 0 | 73 | 18
Increased lymphocytes | 24 | 0 | 13 | 3.1
Decreased lymphocytes | 16 | 1.4 | 56 | 6
Abbreviations: ALT, alanine aminotransferase; AST, aspartate aminotransferase.
aThe denominator used to calculate the rate varied from 70 to 73 in D + T arm and 9 to 33 in C + V arm based on the number of patients with a baseline value and at least one post-treatment value.

6.2 Postmarketing Experience

The following adverse reactions have been identified during post approval use of MEKINIST in combination with dabrafenib. Because these reactions are reported voluntarily from a population of uncertain size, it is not always possible to reliably estimate their frequency or establish a causal relationship to drug exposure.

Cardiac: Atrioventricular block complete. This adverse reaction was also observed with MEKINIST monotherapy.

Immune System: Hemophagocytic lymphohistiocytosis (HLH) [see Warnings and Precautions (5.12)]

Skin and Subcutaneous Tissue: SCAR (including DRESS and SJS) [see Warnings and Precautions (5.9)]

7 DRUG INTERACTIONS

MEKINIST is indicated for use in combination with dabrafenib. Refer to the dabrafenib prescribing information for additional risk information that applies to combination use treatment.

8 USE IN SPECIFIC POPULATIONS

8.1 Pregnancy

Risk Summary

Based on its mechanism of action [see Clinical Pharmacology (12.1)] and findings from animal reproduction studies, MEKINIST can cause fetal harm when administered to a pregnant woman. There is insufficient data in pregnant women exposed to MEKINIST to assess the risks. Trametinib was embryotoxic and abortifacient in rabbits at doses greater than or equal to those resulting in exposures approximately 0.3 times the human exposure at the recommended adult clinical dose (see Data). Advise pregnant women of the potential risk to a fetus.

In the U.S. general population, the estimated background risk of major birth defects and miscarriage in clinically recognized pregnancies is 2% to 4% and 15% to 20%, respectively.

Data

Animal Data

In reproductive toxicity studies, administration of trametinib to rats during the period of organogenesis resulted in decreased fetal weights at doses greater than or equal to 0.031 mg/kg/day [approximately 0.3 times the human exposure at the recommended adult dose based on area under the curve (AUC)]. In rats, at a dose resulting in exposures 1.8-fold higher than the human exposure at the recommended adult dose, there was maternal toxicity and an increase in post-implantation loss.

In pregnant rabbits, administration of trametinib during the period of organogenesis resulted in decreased fetal body weight and increased incidence of variations in ossification at doses greater than or equal to 0.039 mg/kg/day (approximately 0.08 times the human exposure at the recommended adult dose based on AUC). In rabbits administered trametinib at 0.15 mg/kg/day (approximately 0.3 times the human exposure at the recommended adult dose based on AUC) there was an increase in post-implantation loss, including total loss of pregnancy, compared with control animals.

8.2 Lactation

Risk Summary

There are no data on the presence of trametinib in human milk, or the effects of trametinib on the breastfed child or on milk production. Because of the potential for serious adverse reactions in breastfed children, advise women not to breastfeed during treatment with MEKINIST and for 4 months following the last dose.

8.3 Females and Males of Reproductive Potential

Pregnancy Testing

Verify pregnancy status in females of reproductive potential prior to initiating MEKINIST.

Contraception

Based on data from animal studies and its mechanism of action, MEKINIST can cause fetal harm when administered to pregnant women [see Use in Specific Populations (8.1)].

Females

Advise female patients of reproductive potential to use effective contraception during treatment with MEKINIST and for 4 months after the last dose.

Males

To avoid potential drug exposure to pregnant partners and female partners of reproductive potential, advise male patients (including those who have had vasectomies) with female partners of reproductive potential to use condoms during treatment with MEKINIST and for 4 months after the last dose.

Infertility

Females

Advise female patients of reproductive potential that MEKINIST may impair fertility. Increased follicular cysts and decreased corpora lutea were observed in female rats at dose exposures equivalent to 0.3 times the human exposure at the recommended adult dose [see Nonclinical Toxicology (13.1)].

8.4 Pediatric Use

BRAF V600E Mutation-Positive Unresectable or Metastatic Solid Tumors and LGG

The safety and effectiveness of MEKINIST in combination with dabrafenib have been established in pediatric patients 1 year of age and older with unresectable or metastatic solid tumors with BRAF V600E mutation who have progressed following prior treatment and have no satisfactory alternative treatment options; or with LGG with BRAF V600E mutation who require systemic therapy. Use of MEKINIST in combination with dabrafenib for these indications is supported by evidence from studies X2101 and G2201 that enrolled 171 patients (1 to < 18 years of age) with BRAF V600 mutation-positive advanced solid tumors, of which 4 (2.3%) patients were 1 to < 2 years of age, 39 (23%) patients were 2 to < 6 years of age, 54 (32%) patients were 6 to < 12 years of age, and 74 (43%) patients were 12 to < 18 years of age [see Adverse Reactions (6.1), Clinical Pharmacology (12.3), Clinical Studies (14.6, 14.7)].

The safety and effectiveness of MEKINIST in combination with dabrafenib have not been established for these indications in pediatric patients less than 1 year old.

The safety and effectiveness of MEKINIST as a single agent in pediatric patients have not been established.

Juvenile Animal Toxicity Data

In a repeat-dose toxicity study in juvenile rats, decreased bone length and corneal dystrophy were observed at doses resulting in exposures as low as 0.3 times the human exposure at the recommended adult dose based on AUC. Additionally, a delay in sexual maturation was noted at doses resulting in exposures as low as 1.6 times the human exposure at the recommended adult dose based on AUC.

8.5 Geriatric Use

Of the 214 patients with melanoma who received single agent MEKINIST in the METRIC study, 27% were aged 65 years and older and 4% were over 75 years old [see Clinical Studies (14.1)]. This study of single agent MEKINIST in melanoma did not include sufficient numbers of geriatric patients to determine whether they respond differently from younger adults.

Of the 994 patients with melanoma who received MEKINIST plus dabrafenib in the COMBI-d, COMBI-v, and COMBI-AD studies [see Clinical Studies (14.1, 14.2)], 21% were aged 65 years and older and 5% were aged 75 years and older. No overall differences in the effectiveness of MEKINIST plus dabrafenib were observed in geriatric patients as compared to younger adults across these melanoma studies. The incidences of peripheral edema (26% vs. 12%) and anorexia (21% vs. 9%) increased in geriatric patients as compared to younger adults in these studies.

Of the 93 patients with NSCLC who received MEKINIST in Study BRF113928, there were insufficient numbers of geriatric patients aged 65 years and older to determine whether they respond differently from younger adults [see Clinical Studies (14.4)].

Of the 26 patients with ATC who received MEKINIST in Study BRF117019, 77% were aged 65 years and older and 31% were aged 75 years and older [see Clinical Studies (14.4)]. This study in ATC did not include sufficient numbers of younger adults to determine whether they respond differently compared to geriatric patients.

8.6 Hepatic Impairment

No dose adjustment is recommended in patients with mild (bilirubin ≤ upper limit of normal (ULN) and aspartate aminotransferase (AST) > ULN or bilirubin > 1x to 1.5x ULN and any AST) hepatic impairment.

A recommended dosage of MEKINIST has not been established for patients with moderate (bilirubin > 1.5x to 3x ULN and any AST) or severe (bilirubin > 3x to 10x ULN and any AST) hepatic impairment. Consider the risk-benefit profile of MEKINIST related to dosing prior to determining whether to administer MEKINIST to patients with moderate or severe hepatic impairment.

In patients with moderate hepatic impairment, 3 patients who received a starting dose of 1.5 mg orally once daily and two patients who received a starting dose of 2 mg orally once daily did not experience dose limiting toxicities (DLTs) during the first cycle of therapy.

In patients with severe hepatic impairment, 3 patients who received a starting dose of 1 mg orally once daily did not experience DLTs during the first cycle; one patient who received a starting dose of 1.5 mg orally once daily experienced a DLT (grade 3 acneiform rash).

Compared to patients with normal hepatic function, there was no increase in exposure of trametinib in patients with moderate or severe hepatic impairment [see Clinical Pharmacology (12.3)].

10 OVERDOSAGE

The highest doses of MEKINIST evaluated in clinical trials were 4 mg orally once daily and 10 mg administered orally once daily on 2 consecutive days followed by 3 mg once daily. In seven patients treated on one of these two schedules, there were two cases of RPEDs for an incidence of 28%.

Since trametinib is highly bound to plasma proteins, hemodialysis is likely to be ineffective in the treatment of overdose with MEKINIST.

11 DESCRIPTION

Trametinib dimethyl sulfoxide is a kinase inhibitor. The chemical name is acetamide, N-[3-[3-cyclopropyl-5-[(2-fluoro-4- iodophenyl)amino]-3,4,6,7-tetrahydro-6,8-dimethyl- 2,4,7-trioxopyrido[4,3-d]pyrimidin-1(2H)-yl]phenyl]-, compound with 1,1’-sulfinylbis[methane] (1:1). It has a molecular formula C26H23FIN5O4•C2H6OS with a molecular mass of 693.53 g/mol. Trametinib dimethyl sulfoxide has the following chemical structure:

Trametinib dimethyl sulfoxide is a white to almost white powder. It is practically insoluble in the pH range of 2 to 8 in aqueous media.

MEKINIST (trametinib) tablets for oral use are supplied as 0.5 mg and 2 mg tablets for oral administration. Each 0.5 mg tablet contains 0.5635 mg trametinib dimethyl sulfoxide equivalent to 0.5 mg of trametinib non-solvated parent. Each 2 mg tablet contains 2.254 mg trametinib dimethyl sulfoxide equivalent to 2 mg of trametinib non-solvated parent.

The inactive ingredients of MEKINIST tablets are: Tablet Core: colloidal silicon dioxide, croscarmellose sodium, hypromellose, magnesium stearate (vegetable source), mannitol, microcrystalline cellulose, and sodium lauryl sulfate. Coating: hypromellose, iron oxide red (2 mg tablets), iron oxide yellow (0.5 mg tablets), polyethylene glycol, polysorbate 80 (2 mg tablets), and titanium dioxide.

MEKINIST (trametinib) for oral solution is a white or almost white powder which produces a clear colorless solution when reconstituted with water. Each bottle contains 4.7 mg of trametinib equivalent to 5.3 mg trametinib dimethyl sulfoxide. Each mL of reconstituted trametinib solution contains 0.05 mg of trametinib non-solvated parent. The inactive ingredients of MEKINIST for oral solution are betadex sulfobutyl ether sodium, citric acid monohydrate, dibasic sodium phosphate, methylparaben, potassium sorbate, sucralose, and strawberry flavor.

12 CLINICAL PHARMACOLOGY

12.1 Mechanism of Action

Trametinib is a reversible inhibitor of mitogen-activated extracellular signal-regulated kinase 1 (MEK1) and MEK2 activation and of MEK1 and MEK2 kinase activity. MEK proteins are upstream regulators of the extracellular signal-related kinase (ERK) pathway, which promotes cellular proliferation. BRAF V600E mutations result in constitutive activation of the BRAF pathway which includes MEK1 and MEK2. Trametinib inhibits cell growth of various BRAF V600 mutation-positive tumors in vitro and in vivo.

Trametinib and dabrafenib target two different kinases in the RAS/RAF/MEK/ERK pathway. Use of trametinib and dabrafenib in combination resulted in greater growth inhibition of BRAF V600 mutation-positive tumor cell lines in vitro and prolonged inhibition of tumor growth in BRAF V600 mutation-positive tumor xenografts compared with either drug alone.

In the setting of BRAF-mutant colorectal cancer, induction of EGFR-mediated MAPK pathway re-activation has been identified as a mechanism of intrinsic resistance to BRAF inhibitors [see Indications and Usage (1.7)].

12.2 Pharmacodynamics

Administration of MEKINIST tablets 1 mg and 2 mg to patients with BRAF V600 mutation-positive melanoma resulted in dose-dependent changes in tumor biomarkers, including inhibition of phosphorylated ERK, inhibition of Ki67 (a marker of cell proliferation), and increases in p27 (a marker of apoptosis).

Cardiac Electrophysiology

The heart rate-corrected QT (QTc) prolongation potential of trametinib was assessed in a dedicated study in 32 patients who received placebo on Day 1 and MEKINIST tablets 2 mg once daily on Days 2-14 followed by MEKINIST tablets 3 mg on Day 15. No large changes in the mean QTc interval (i.e., > 20 ms) were detected in the study.

A decrease from baseline in HR by 9 beats/min (90% CI: -11.4 to -6.1) and an increase from baseline in PR by 20 ms (90% CI: 13.0 to 27.4) relative to placebo was observed at two hours post-dose in the same study.

In clinical trials in patients who received MEKINIST with dabrafenib, QTc prolongation > 500 ms occurred in 0.8% of patients and QTc increased by > 60 ms from baseline in 3.8% of patients.

12.3 Pharmacokinetics

The pharmacokinetics of trametinib were characterized following a single dose and multiple doses in patients with solid tumors and BRAF V600 mutation-positive metastatic melanoma. Following administration of MEKINIST tablets 0.125 mg (0.0625 times the approved recommended adult dosage) to 4 mg (2 times the approved recommended adult dosage) daily, both Cmax and AUC increase proportionally with dose. Intersubject variability in AUC and Cmax at steady state is 22% and 28%, respectively.

Absorption

The median time to achieve peak plasma concentrations (Tmax) is 1.5 hours post-dose. The mean absolute bioavailability of MEKINIST tablets is 72% and MEKINIST for oral solution is 81%.

Effect of Food

Following administration of MEKINIST tablets, a high-fat, high-calorie meal (approximately 1000 calories) decreased trametinib AUC by 24%, Cmax by 70%, and delayed Tmax by approximately 4 hours as compared with fasted conditions.

Administration of a single 2 mg dose of MEKINIST for oral solution with a low-fat, low-calorie meal (approximately 500 calories, 14 grams fat, 80 grams carbohydrates, and 12 grams protein) showed no clinically significant changes on both AUC and Cmax of trametinib as compared with fasted conditions.

Distribution

Trametinib is 97.4% bound to human plasma proteins. The apparent volume of distribution (Vc/F) is 214 L.

Elimination

The estimated elimination half-life is 3.9 to 4.8 days. The apparent clearance is 4.9 L/h.

Metabolism

Trametinib is metabolized predominantly via deacetylation alone or with mono-oxygenation or in combination with glucuronidation biotransformation pathways in vitro. Deacetylation is mediated by carboxylesterases (i.e., carboxylesterase 1b/c and 2) and may also be mediated by other hydrolytic enzymes.

Following a single dose of [^14C]-trametinib, approximately 50% of circulating radioactivity is represented as the parent compound; however, ≥ 75% of drug-related material in plasma is the parent compound based on metabolite profiling after repeat dosing of trametinib.

Excretion

Following oral administration of [^14C]-trametinib, greater than 80% of excreted radioactivity was recovered in the feces while less than 20% of excreted radioactivity was recovered in the urine with less than 0.1% of the excreted dose as parent.

Specific Populations

Age (18 to 93 years), sex, body weight (36 to 170 kg), and renal impairment (eGFR 15 to 89 mL/min/1.73 m^2) have no clinically significant effect on the exposure of trametinib. There are insufficient data to evaluate potential differences in the exposure of trametinib by race or ethnicity.

Pediatric Patients: The pharmacokinetics of trametinib in glioma and other solid tumors were evaluated in 244 patients aged 1 to < 18 years following a single dose or multiple doses. Pharmacokinetic parameters in patients aged 1 to < 18 years are within range of values previously observed in adults given the same dose based on weight. Weight (6 to 156 kg) was found to have a statistically significant effect on trametinib oral clearance in this population.

Patients with Hepatic Impairment: Hepatic impairment (defined by bilirubin and AST levels) had no significant effect in trametinib exposure or apparent drug clearance compared with patients with normal hepatic function.

Drug Interaction Studies

Effect of Dabrafenib on Trametinib: Coadministration of MEKINIST tablets 2 mg daily with dabrafenib resulted in no change in AUC of trametinib.

Effect of Trametinib on CYP Substrates: Coadministration of MEKINIST tablets 2 mg once daily with a sensitive CYP3A4 substrate had no clinically relevant effect on the AUC and Cmax of the sensitive CYP3A4 substrate.

Based on in vitro studies, trametinib is an inhibitor of CYP2C8, but is not an inhibitor of CYP1A2, CYP2A6, CYP2B6, CYP2C9, CYP2C19, or CYP2D6 at a clinically relevant systemic concentration.

Effect of Transporters on Trametinib: Trametinib is a substrate of P-glycoprotein (P-gp) and BSEP. Inhibition of P-gp is unlikely to result in a clinically important increase in trametinib concentrations as trametinib exhibits high passive permeability and bioavailability. Trametinib is not a substrate of BCRP, OATP1B1, OATP1B3, OATP2B1, OCT1, MRP2, or MATE1 in vitro.

Effect of Trametinib on Transporters: Based on in vitro studies, trametinib is not an inhibitor of P-gp, BCRP, OATP1B1, OATP1B3, OAT1, OAT3, OCT2, BSEP, MRP2, or MATE1 at a clinically relevant systemic concentration.

13 NONCLINICAL TOXICOLOGY

13.1 Carcinogenesis, Mutagenesis, Impairment of Fertility

Carcinogenicity studies with trametinib have not been conducted. Trametinib was not genotoxic in studies evaluating reverse mutations in bacteria, chromosomal aberrations in mammalian cells, and micronuclei in the bone marrow of rats.

Trametinib may impair fertility in humans. In female rats given trametinib for up to 13 weeks, increased follicular cysts and decreased corpora lutea were observed at doses ≥ 0.016 mg/kg/day (approximately 0.3 times the human exposure at the recommended adult dose based on AUC). In rat and dog toxicity studies up to 13 weeks in duration, there were no treatment effects observed on male reproductive tissues [see Use in Specific Populations (8.3)].

14 CLINICAL STUDIES

14.1 BRAF V600E or V600K Mutation-Positive Unresectable or Metastatic Melanoma

MEKINIST as a Single Agent

The safety and efficacy of MEKINIST were evaluated in an international, multi-center, randomized (2:1), open-label, active-controlled trial (the METRIC study; NCT01245062) in 322 patients with BRAF V600E or V600K mutation-positive, unresectable or metastatic melanoma. In the METRIC study, patients were not permitted to have more than one prior chemotherapy regimen for advanced or metastatic disease; prior treatment with a BRAF inhibitor or MEK inhibitor was not permitted. Patients were randomized to receive MEKINIST 2 mg orally once daily (N = 214) or chemotherapy (N = 108) consisting of either dacarbazine 1000 mg/m^2 intravenously every 3 weeks or paclitaxel 175 mg/m^2 intravenously every 3 weeks. Treatment continued until disease progression or unacceptable toxicity. Randomization was stratified according to prior use of chemotherapy for advanced or metastatic disease (yes vs. no) and LDH level (normal vs. greater than ULN). Tumor tissue was evaluated for BRAF mutations at a central testing site using a clinical trial assay. Tumor samples from 289 patients (196 patients treated with MEKINIST and 93 chemotherapy-treated patients) were also tested retrospectively using an FDA-approved companion diagnostic test, THxID®-BRAF assay. The major efficacy outcome measure was progression-free survival (PFS) as assessed by the investigator.

The median age for randomized patients was 54 years, 54% were male, greater than 99% were White, and all patients had baseline ECOG performance status of 0 or 1. Most patients had metastatic disease (94%), had M1c disease (64%), had elevated LDH (36%), had no history of brain metastasis (97%), and received no prior chemotherapy for advanced or metastatic disease (66%). The distribution of BRAF V600 mutations was BRAF V600E (87%), V600K (12%), or both (less than 1%). The median durations of follow-up prior to initiation of alternative treatment were 4.9 months for patients treated with MEKINIST and 3.1 months for patients treated with chemotherapy. Fifty-one (47%) patients crossed over from the chemotherapy arm at the time of disease progression to receive MEKINIST.

The METRIC study demonstrated a statistically significant increase in PFS in the patients treated with MEKINIST. Table 20 and Figure 1 summarize the PFS results.

Table 20. Efficacy Results in the METRIC Study
Investigator-Assessed Endpoints | MEKINIST N = 214 | Chemotherapy N = 108
Progression-Free Survival
Number of events (%) | 117 (55%) | 77 (71%)
Progressive disease | 107 (50%) | 70 (65%)
Death | 10 (5%) | 7 (6%)
Median, months (95% CI) | 4.8 (4.3, 4.9) | 1.5 (1.4, 2.7)
HRa (95% CI) | 0.47 (0.34, 0.65)
P-value (log-rank test) | < 0.0001
Confirmed Tumor Responses
Overall response rate (95% CI) | 22% (17%, 28%) | 8% (4%, 15%)
Complete response, n (%) | 4 (2%) | 0
Partial response, n (%) | 43 (20%) | 9 (8%)
Duration of Response
Median DoR, months (95% CI) | 5.5 (4.1, 5.9) | NR (3.5, NR)
Abbreviations: CI, confidence interval; DoR, duration of response; HR, hazard ratio; NR, not reached.
aPike estimator.

Figure 1. Kaplan-Meier Curves of Investigator-Assessed Progression-Free Survival (ITT Population) in the METRIC Study

In supportive analyses based on independent radiologic review committee (IRRC) assessment, the PFS results were consistent with those of the primary efficacy analysis.

MEKINIST with Dabrafenib

COMBI-d Study

The safety and efficacy of MEKINIST administered with dabrafenib were evaluated in an international, randomized, double-blind, active-controlled trial (the COMBI-d study; NCT01584648). The COMBI-d study compared dabrafenib plus MEKINIST to dabrafenib plus placebo as first-line treatment for patients with unresectable (Stage IIIC) or metastatic (Stage IV) BRAF V600E or V600K mutation-positive cutaneous melanoma. Patients were randomized (1:1) to receive MEKINIST 2 mg once daily plus dabrafenib 150 mg twice daily or dabrafenib 150 mg twice daily plus matching placebo. Randomization was stratified by LDH level (> ULN vs. ≤ ULN) and BRAF mutation subtype (V600E vs. V600K). The major efficacy outcome measure was investigator-assessed progression-free survival (PFS) per RECIST v1.1 with additional efficacy outcome measures of overall survival (OS) and confirmed overall response rate (ORR).

In the COMBI-d study, 423 patients were randomized to MEKINIST plus dabrafenib (n = 211) or dabrafenib plus placebo (n = 212). The median age was 56 years (range: 22 to 89), 53% were male, > 99% were White, 72% had ECOG performance status of 0, 4% had Stage IIIC, 66% had M1c disease, 65% had normal LDH, and 2 patients had a history of brain metastases. All patients had tumor containing BRAF V600E or V600K mutations as determined by centralized testing with the FDA-approved companion diagnostic test; 85% had BRAF V600E mutation-positive melanoma and 15% had BRAF V600K mutation-positive melanoma.

The COMBI-d study demonstrated statistically significant improvements in PFS and OS. Table 21 and Figure 2 summarize the efficacy results.

Table 21. Efficacy Results in the COMBI-d Study
Endpoint | MEKINIST plus Dabrafenib N = 211 | Placebo plus Dabrafenib N = 212
Progression-Free Survivala
Number of events (%) | 102 (48%) | 109 (51%)
Median, months (95% CI) | 9.3 (7.7, 11.1) | 8.8 (5.9, 10.9)
HR (95% CI) | 0.75 (0.57, 0.99)
P-valueb | 0.035
Overall Survival
Number of deaths (%) | 99 (47%) | 123 (58%)
Median, months (95% CI) | 25.1 (19.2, NR) | 18.7 (15.2, 23.1)
HR (95% CI) | 0.71 (0.55, 0.92)
P-valueb | 0.01
Overall Response Ratea
ORR (95% CI) | 66% (60%, 73%) | 51% (44%, 58%)
P-value | < 0.001
Complete response | 10% | 8%
Partial response | 56% | 42%
Median DoR, months (95% CI) | 9.2 (7.4, NR) | 10.2 (7.5, NR)
Abbreviations: CI, confidence interval; DoR, duration of response; HR, hazard ratio; NR, not reached; ORR, overall response rate.
aPFS and ORR were assessed by investigator.
bBased on stratified log-rank test.

Figure 2. Kaplan-Meier Curves of Overall Survival in the COMBI-d Study

COMBI-MB Study

The activity of MEKINIST with dabrafenib for the treatment of BRAF V600E or V600K mutation-positive melanoma, metastatic to the brain, was evaluated in a non-randomized, open-label, multi-center, multi-cohort trial (the COMBI-MB study; NCT02039947). Eligible patients were required to have at least one measurable intracranial lesion and to have no leptomeningeal disease, parenchymal brain metastasis greater than 4 cm in diameter, ocular melanoma, or primary mucosal melanoma. Patients received MEKINIST 2 mg orally once daily and dabrafenib 150 mg orally twice daily until disease progression or unacceptable toxicity. The major efficacy outcome measure was intracranial response rate, defined as the percentage of patients with a confirmed intracranial response per RECIST v1.1, modified to allow up to five intracranial target lesions at least 5 mm in diameter, as assessed by independent review.

The COMBI-MB study enrolled 121 patients with a BRAF V600E (85%) or V600K (15%) mutation. The median age was 54 years (range: 23 to 84), 58% were male, 100% were White, 8% were from the United States, 65% had normal LDH at baseline, and 97% had an ECOG performance status of 0 or 1. Intracranial metastases were asymptomatic in 87% and symptomatic in 13% of patients, 22% received prior local therapy for brain metastases, and 87% also had extracranial metastases.

The intracranial response rate was 50% (95% CI: 40, 60), with a complete response rate of 4.1% and a partial response rate of 46%. The median duration of intracranial response was 6.4 months (range: 1 to 31). Of the patients with an intracranial response, 9% had stable or progressive disease as their best overall response.

14.2 Adjuvant Treatment of BRAF V600E or V600K Mutation-Positive Melanoma

The efficacy of MEKINIST administered with dabrafenib was evaluated in an international, multi-center, randomized, double-blind, placebo-controlled trial (COMBI-AD; NCT01682083) that enrolled patients with Stage III melanoma with BRAF V600E or V600K mutations as detected by the THxID®-BRAF assay and pathologic involvement of regional lymph node(s). Enrollment required complete resection of melanoma with complete lymphadenectomy within 12 weeks prior to randomization. The trial excluded patients with mucosal or ocular melanoma, unresectable in-transit metastases, distant metastatic disease, or prior systemic anti-cancer treatment, including radiotherapy. Patients were randomized (1:1) to receive MEKINIST 2 mg once daily in combination with dabrafenib 150 mg twice daily or two placebos for up to 1 year. Randomization was stratified by BRAF mutation status (V600E or V600K) and American Joint Committee on Cancer (AJCC; 7th Edition) Stage (IIIA, IIIB, or IIIC). The major efficacy outcome measure was relapse-free survival (RFS), defined as the time from randomization to disease recurrence (local, regional, or distant metastasis), new primary melanoma, or death from any cause, whichever occurred first as assessed by the investigator. Patients underwent imaging for tumor recurrence every 3 months for the first two years and every 6 months thereafter.

In COMBI-AD, a total of 870 patients were randomized: 438 to MEKINIST in combination with dabrafenib and 432 to placebo. Median age was 51 years (range: 18 to 89), 55% were male, 99% were White, and 91% had an ECOG performance status of 0. Disease characteristics were AJCC Stage IIIA (18%), Stage IIIB (41%), Stage IIIC (40%), stage unknown (1%); BRAF V600E mutation (91%), BRAF V600K mutation (9%); macroscopic lymph nodes (65%); and tumor ulceration (41%).

The median duration of follow-up at the time of the primary analysis was 2.8 years.

COMBI-AD showed a statistically significant improvement in RFS in patients randomized to MEKINIST in combination with dabrafenib compared to those randomized to placebo. Efficacy results are presented in Table 22 and Figure 3.

Table 22. Efficacy Results in COMBI-AD in the Adjuvant Treatment of Melanoma
Investigator-Assessed Endpoint | MEKINIST plus Dabrafenib N = 438 | Placebo N = 432
Relapse-Free Survival
Number of events (%) | 166 (38) | 248 (57)
Median, months (95% CI) | NE (44.5, NE) | 16.6 (12.7, 22.1)
HR (95% CI)a | 0.47 (0.39, 0.58)
P-valueb | < 0.0001
Abbreviations: HR, hazard ratio; CI, confidence interval; NE, not estimable.
aPike estimator obtained from the stratified log-rank test.
bLog-rank test stratified by disease stage (IIIA vs. IIIB vs. IIIC) and BRAF V600 mutation type (V600E vs. V600K).

Figure 3. Kaplan-Meier Curves for Investigator-Assessed Relapse-Free Survival in COMBI-AD in the Adjuvant Treatment of Melanoma

The median duration of follow-up at the time of the final overall survival analysis was 8.0 years. The estimated hazard ratio for overall survival was 0.80 (95% CI: 0.62, 1.01; p=0.063) with 125 events (29%) in the combination arm and 136 events (31%) in the placebo arm. Median overall survival was not estimable in both arms.

14.3 BRAF V600E Mutation-Positive Metastatic Non-Small Cell Lung Cancer

The safety and efficacy of dabrafenib alone or administered with MEKINIST were evaluated in a multi-center, three-cohort, non-randomized, activity-estimating, open-label trial (Study BRF113928; NCT01336634). Key eligibility criteria were locally confirmed BRAF V600E mutation-positive metastatic NSCLC, no prior exposure to BRAF or MEK inhibitor, and absence of EGFR mutation or ALK rearrangement (unless patients had progression on prior tyrosine kinase inhibitor therapy). Patients enrolled in Cohorts A and B were required to have received at least one previous platinum-based chemotherapy regimen for NSCLC with demonstrated disease progression but no more than three prior systemic regimens. Patients in Cohort C could not have received prior systemic therapy for metastatic NSCLC. Patients in Cohort A received dabrafenib 150 mg twice daily. Patients in Cohorts B and C received MEKINIST 2 mg once daily and dabrafenib 150 mg twice daily. The major efficacy outcome measure was overall response rate (ORR) per RECIST v1.1 as assessed by independent review committee (IRC) and duration of response (DoR).

There were a total of 171 patients enrolled which included 78 patients enrolled in Cohort A, 57 patients enrolled in Cohort B, and 36 patients enrolled in Cohort C. The characteristics of the study population were: a median age of 66 years; 48% male; 81% White, 14% Asian, 3% Black, and 2% Hispanic; 60% former smokers, 32% never smokers, and 8% current smokers; 27% had ECOG performance status (PS) of 0, 63% had ECOG PS of 1, and 11% had ECOG PS of 2; 99% had metastatic disease of which 6% had brain metastasis at baseline and 14% had liver metastasis at baseline; 11% had systemic anti-cancer therapy in the adjuvant setting and 58% of the 135 previously treated patients had only one line of prior systemic therapy for metastatic disease; 98% had non-squamous histology.

Efficacy results are summarized in Table 23.

Table 23. Efficacy Results Based on Independent Review in Study BRF113928
Treatment | Dabrafenib | MEKINIST plus Dabrafenib
Population | Previously Treated N = 78 | Previously Treated N = 57 | Treatment Naïve N = 36
Overall Response Ratea
ORR (95% CI) | 27% (18%, 38%) | 61% (48%, 74%) | 61% (44%, 77%)
Complete response | 1% | 5% | 8%
Partial response | 26% | 56% | 53%
Duration of Responsea | n = 21 | n = 35 | n = 22
Median DoR, months (95% CI) | 18.0 (4.2, 40.1) | 9.0 (5.8, 26.2) | 15.2 (7.8, 23.5)
Abbreviations: CI, confidence interval; DoR, duration of response; ORR, overall response rate.
aRepresents final analysis results (cutoff date of 24 Feb 2021) for the primary analysis responder cohorts.

In a subgroup analysis of patients with retrospectively centrally confirmed BRAF V600E mutation-positive NSCLC with the Oncomine™ Dx Target Test, the ORR results were similar to those presented in Table 23.

14.4 BRAF V600E Mutation-Positive Locally Advanced or Metastatic Anaplastic Thyroid Cancer

The safety and efficacy of MEKINIST administered with dabrafenib was evaluated in an activity-estimating, nine-cohort, multi-center, non-randomized, open-label trial (Study BRF117019; NCT02034110) in patients with rare cancers with the BRAF V600E mutation, including locally advanced, unresectable, or metastatic ATC with no standard locoregional treatment options. Trial BRF117019 excluded patients who could not swallow or retain the medication; who received prior treatment with BRAF or MEK inhibitors; with symptomatic or untreated CNS metastases; or who had airway obstruction. Patients received MEKINIST 2 mg once daily and dabrafenib 150 mg twice daily. The major efficacy outcome measure was overall response rate (ORR) per RECIST v1.1 as assessed by independent review committee (IRC) and duration of response (DoR).

Thirty-six patients were enrolled and were evaluable for response in the ATC cohort. The median age was 71 years (range: 47 to 85); 44% were male, 50% White, 44% Asian; and 94% had ECOG performance status of 0 or 1. Prior anti-cancer treatments included surgery and external beam radiotherapy (83% each), and systemic therapy (67%).

Efficacy results are summarized in Table 24.

Table 24. Efficacy Results in the ATC Cohort Based on Independent Review of Study BRF117019
ATC Cohort Population | N = 36
Overall Response Rate
ORR (95% CI) | 53% (35.5%, 69.6%)
Complete response | 6%
Partial response | 47%
Duration of Response | n = 19
Median DoR, months (95% CI) | 13.6 (3.8, NE)
% with DoR ≥ 6 months | 68%
% with DoR ≥ 12 months | 53%
Abbreviations: ATC, anaplastic thyroid cancer; CI, confidence interval; DoR, duration of response; NE, not estimable; ORR, overall response rate.

14.5 Lack of Clinical Activity in Metastatic Melanoma Following BRAF-Inhibitor Therapy

The clinical activity of MEKINIST as a single agent was evaluated in a single-arm, multi-center, international trial in 40 patients with BRAF V600E or V600K mutation-positive, unresectable or metastatic melanoma who had received prior treatment with a BRAF inhibitor. All patients received MEKINIST at a dose of 2 mg orally once daily until disease progression or unacceptable toxicity.

The median age was 58 years, 63% were male, all were White, 98% had baseline ECOG PS of 0 or 1, and the distribution of BRAF V600 mutations was V600E (83%), V600K (10%), and the remaining patients had multiple V600 mutations (5%), or unknown mutational status (2%). No patient achieved a confirmed partial or complete response as determined by the clinical investigators.

14.6 BRAF V600E Mutation-Positive Unresectable or Metastatic Solid Tumors

The safety and efficacy of MEKINIST in combination with dabrafenib for the treatment of BRAF V600E mutation-positive unresectable or metastatic solid tumors were evaluated in Trials BRF117019, NCI-MATCH, and CTMT212X2101, and supported by results in COMBI-d, COMBI-v [see Clinical Studies (14.2)], and BRF113928 [see Clinical Studies (14.4)]. In adult studies, patients received MEKINIST 2 mg once daily and dabrafenib 150 mg twice daily. The major efficacy outcome measures were ORR per RECIST v1.1, RANO [HGG] or modified RANO [LGG] criteria and duration of response (DoR).

BRF117019 Study and NCI-MATCH Study

Study BRF117019 (NCT02034110) [see Clinical Studies (14.5)] is a multi-cohort, multi-center, non-randomized, open-label trial in adult patients with selected tumors with the BRAF V600E mutation, including high-grade glioma (HGG) (n = 45), biliary tract cancer (BTC) (n = 43), low-grade glioma (LGG) (n = 13), adenocarcinoma of small intestine (ASI) (n = 3), gastrointestinal stromal tumor (GIST) (n = 1), and anaplastic thyroid cancer [see Clinical Studies (14.5)]. Patients were enrolled based on local assessments of BRAF V600E mutation status; a central laboratory confirmed the BRAF V600E mutation in 93 of 105 patients.

Arm H (EAY131-H) of the NCI-MATCH study (NCT02465060) is a single-arm, open-label study that enrolled patients with a BRAF V600E mutation. Patients with melanoma, thyroid cancer, or CRC were excluded. BRAF V600E mutation status for enrollment was determined either by central or local laboratory test. The study included adult patients with solid tumors including gastrointestinal tumors (n = 14), lung tumors (n = 7), gynecologic or peritoneal tumors (n = 6), CNS tumors (n = 4), and ameloblastoma of mandible (n = 1).

Among the 131 patients enrolled in BRF117019 and NCI-MATCH with the tumor types shown in Table 25, the baseline characteristics were: median age of 51 years with 20% age 65 or older; 56% female; 85% White, 9% Asian, 3% Black, 3% other; and 37% ECOG PS of 0, 56% ECOG PS of 1, and 6% ECOG PS of 2. Of the 131 patients, 90% received prior systemic therapy.

Efficacy results in patients with solid tumors are summarized in Table 25.

Table 25. Efficacy Results Based on Independent Review in Study BRF117019 and NCI-MATCH Arm H
Tumor Typea | N | Objective Response Rate |  | Duration of Response
 |  | % | 95% CI | Range (months)
Biliary tract cancerb | 48 | 46 | (31, 61) | 1.8d, 40d
High-grade gliomac | 48 | 33 | (20, 48) | 3.9, 44
Glioblastoma | 32 | 25 | (12, 43) | 3.9, 27
Anaplastic pleomorphic xanthoastrocytoma | 6 | 67 | (22, 96) | 6, 43
Anaplastic astrocytoma | 5 | 20 | (0.5, 72) | 15
Astroblastoma | 2 | 100 | (16, 100) | 15, 23d
Undifferentiated | 1 | PR | (2.5, 100) | 6
Anaplastic ganglioglioma | 1 | 0 | NA | NA
Anaplastic oligodendroglioma | 1 | 0 | NA | NA
Low-grade glioma | 14 | 50 | (23, 77) | 6, 29d
Astrocytoma | 4 | 50 | (7, 93) | 7, 23
Ganglioglioma | 4 | 50 | (7, 93) | 6, 13
Pleomorphic xanthoastrocytoma | 2 | 50 | (1.3, 99) | 6
Pilocytic astrocytoma | 2 | 0 | NA | NA
Choroid plexus papilloma | 1 | PR | (2.5, 100) | 29d
Gangliocytoma/ganglioglioma | 1 | PR | (2.5, 100) | 18d
Low-grade serous ovarian carcinoma | 5 | 80 | (28, 100) | 12, 42d
Adenocarcinoma small intestine | 4 | 50 | (7, 93) | 7, 8
Adenocarcinoma pancreas | 3 | 0 | NA | NA
Mixed ductal/adenoneuroendocrine carcinoma | 2 | 0 | NA | NA
Neuroendocrine carcinoma of colon | 2 | 0 | NA | NA
Ameloblastoma of mandible | 1 | PR | (2.5, 100) | 30
Combined small cell-squamous carcinoma of lung | 1 | PR | (2.5, 100) | 5
Mucinous-papillary serous adenocarcinoma of peritoneum | 1 | PR | (2.5, 100) | 8
Adenocarcinoma of anus | 1 | 0 | NA | NA
Gastrointestinal stromal tumor | 1 | 0 | NA | NA
Abbreviations: NA, not applicable; PR, partial response.
aExcludes NSCLC (n = 6) and ATC (n = 36) (previously approved tumor types for MEKINIST in combination with dabrafenib).
bMedian DoR 9.8 months (95% CI: 5.3, 20.4).
cMedian DoR 13.6 months (95% CI: 5.5, 26.7).
dDenotes a right-censored DoR.

CTMT212X2101 (X2101) Study

Study X2101 (NCT02124772) was a multi-center, open-label, multi-cohort study in pediatric patients with refractory or recurrent solid tumors. Part C was a dose escalation of MEKINIST in combination with dabrafenib in patients with a BRAF V600E mutation. Part D was a cohort expansion phase of MEKINIST in combination with dabrafenib in patients with LGG with a BRAF V600E mutation. The major efficacy outcome measure was ORR as assessed by independent review committee per RANO criteria.

The efficacy of MEKINIST in combination with dabrafenib was evaluated in 48 pediatric patients, including 34 patients with LGG and 2 patients with HGG.

For patients with BRAF V600E mutation-positive LGG and HGG in Parts C and D, the median age was 10 years (range: 1 to 17); 50% were male, 75% White, 8% Asian, 3% Black; and 58% had Karnofsky/Lansky performance status of 100. Prior anti-cancer treatments included surgery (83%), external beam radiotherapy (2.8%), and systemic therapy (92%). The ORR was 25% (95% CI: 12%, 42%). For the 9 patients who responded, DoR was ≥ 6 months for 78% of patients and ≥ 24 months for 44% of patients.

CDRB436G2201 (G2201) Study – High-Grade Glioma Cohort

Study G2201 (NCT02684058) was a multi-center, randomized, open-label, Phase II study of dabrafenib and trametinib in chemotherapy-naïve pediatric patients with BRAF V600E mutant low-grade glioma (LGG) and patients with relapsed or progressive BRAF V600E mutant HGG. Patients with HGG were enrolled in a single-arm cohort. The major efficacy outcome measure for the HGG cohort was ORR as assessed by independent review committee per RANO 2010 criteria.

The efficacy of MEKINIST in combination with dabrafenib was evaluated in 41 pediatric patients with relapsed or progressive HGG.

For patients with BRAF V600E mutant HGG enrolled in the HGG cohort, the median age was 13 years (range: 2 to 17); 56% were female, 61% White, 27% Asian, 2.4% Black, and 37% had Karnofsky/Lansky performance status of 100. Prior anti-cancer treatments included surgery (98%), radiotherapy (90%), and chemotherapy (81%). The ORR was 56% (95% CI: 40, 72). The median DoR was not reached (95% CI: 9.2, NE). For the 23 patients who responded in the HGG cohort, DoR was ≥ 6 months for 78% of patients, ≥ 12 months for 48% of patients, and ≥ 24 months for 22% of patients.

14.7 BRAF V600E Mutation-Positive Low-Grade Glioma

CDRB436G2201 (G2201) Study – Low-Grade Glioma Cohort

The safety and efficacy of MEKINIST in combination with dabrafenib for the treatment of BRAF V600E mutation-positive low-grade glioma (LGG) in pediatric patients aged 1 to < 18 years of age were evaluated in the multi-center, open-label trial (Study CDRB436G2201; NCT02684058). Patients with LGG (WHO grades 1 and 2) who required first systemic therapy were randomized in a 2:1 ratio to dabrafenib plus trametinib (D + T) or carboplatin plus vincristine (C + V).

BRAF mutation status was identified prospectively via a local assessment or a central laboratory test. In addition, retrospective testing of available tumor samples by the central laboratory was performed to evaluate BRAF V600E mutation status.

Patients received age- and weight-based dosing of MEKINIST and dabrafenib until loss of clinical benefit or until unacceptable toxicity. Carboplatin and vincristine were dosed based on body surface area at doses 175 mg/m^2 and 1.5 mg/m^2 (0.05 mg/kg for patients < 12 kg), respectively, as one 10-week induction course followed by eight 6-week cycles of maintenance therapy.

The major efficacy outcome measure was overall response rate (ORR) by independent review based on RANO LGG (2017) criteria. Additional efficacy outcome measures were progression-free survival and overall survival. The primary analysis was performed when all patients had completed at least 32 weeks of therapy.

In the LGG cohort, 110 patients were randomized to D + T (n = 73) or C + V (n = 37). Median age was 9.5 years (range: 1 to 17); 60% were female. Study G2201 showed a statistically significant improvement in ORR and PFS in patients with LGG randomized to D + T compared to those randomized to C + V. Efficacy results are shown in Table 26.

Table 26. Efficacy Results Based on Independent Review in Study G2201 (LGG cohort)
 | MEKINIST plus Dabrafenib N = 73 | Carboplatin plus Vincristine N = 37
Overall Response Rate
ORR% (95% CI)a | 46.6 (34.8, 58.6) | 10.8 (3.0, 25.4)
P-value | < 0.001
Complete response, n (%) | 2 (2.7) | 1 (2.7)
Partial response, n (%) | 32 (44) | 3 (8)
Duration of Response
Median (95% CI)b, months | 23.7 (14.5, NE) | NE (6.6, NE)
% with observed DoR ≥ 12 months | 56 | 50
% with observed DoR ≥ 24 months | 15 | 25
Progression-Free Survival
Median (95% CI)b, months | 20.1 (12.8, NE) | 7.4 (3.6, 11.8)
Hazard ratio (95% CI)c | 0.31 (0.17, 0.55)
P-value | < 0.001
Abbreviations: CI, confidence interval; NE, not estimable.
aBased on Clopper-Pearson exact confidence interval
bBased on Kaplan-Meier method
cBased on proportional hazards model

Figure 4. Kaplan-Meier Curves for Progression-Free Survival in Study G2201 (LGG cohort)

At the time of the interim analysis of overall survival (OS), conducted when all patients had completed at least 32 weeks of treatment or had discontinued earlier, there was one death on the C + V arm. The OS results at interim analysis did not reach statistical significance.

16 HOW SUPPLIED/STORAGE AND HANDLING

MEKINIST Tablets:

0.5 mg tablets: Yellow, ovaloid, biconvex, unscored film-coated tablets with beveled edges and with the Novartis logo debossed on one side and ‘TT’ on the other side; available in bottles of 30 (NDC 0078-1105-15).

2 mg tablets: Pink, round, biconvex, unscored film-coated tablets with beveled edges and with the Novartis logo debossed on one side and ‘LL’ on the other side; available in bottles of 30 (NDC 0078-1112-15).

Store at 20°C to 25°C (68°F to 77°F); excursions permitted between 15°C and 30°C (59°F and 86°F) [see USP Controlled Room Temperature]. Dispense in original bottle. Do not remove desiccant. Protect from moisture and light. Do not place medication in pill boxes.

MEKINIST for Oral Solution:

White or almost white powder in amber glass bottles, co-packaged with a press-in bottle adapter and an oral syringe. Each bottle contains 4.7 mg of trametinib equivalent to 5.3 mg trametinib dimethyl sulfoxide. Each mL of reconstituted strawberry flavored trametinib solution contains 0.05 mg of trametinib non-solvated parent. (NDC 0078-1161-47).

Store refrigerated at 2°C to 8°C (36°F to 46°F). Store in the original carton to protect from light and moisture.

After reconstitution, store in the original bottle below 25°C (77°F) and do not freeze.

Discard any unused solution 35 days after reconstitution.

17 PATIENT COUNSELING INFORMATION

Advise the patient to read the FDA-approved patient labeling (Patient Information and Instructions for Use).

New Primary Cutaneous and Non-cutaneous Malignancies

Advise patients that MEKINIST administered with dabrafenib can result in the development of new primary cutaneous and non-cutaneous malignancies. Advise patients to contact their healthcare provider immediately for any new lesions, changes to existing lesions on their skin, or other signs and symptoms of malignancies [see Warnings and Precautions (5.1)].

Hemorrhage

Advise patients that MEKINIST administered with dabrafenib increases the risk of intracranial and gastrointestinal hemorrhage. Advise patients to contact their healthcare provider to seek immediate medical attention for signs or symptoms of unusual bleeding or hemorrhage [see Warnings and Precautions (5.2)].

Colitis and Gastrointestinal Perforation

Advise patients that MEKINIST can cause colitis and gastrointestinal perforation and to contact their healthcare provider for signs or symptoms of colitis or gastrointestinal perforation [see Warnings and Precautions (5.3)].

Venous Thromboembolic Events

Advise patients that MEKINIST administered with dabrafenib increases the risks of PE and DVT. Advise patients to seek immediate medical attention for sudden onset of difficulty breathing, leg pain, or swelling [see Warnings and Precautions (5.4)].

Cardiomyopathy

Advise patients that MEKINIST can cause cardiomyopathy and to immediately report any signs or symptoms of heart failure to their healthcare provider [see Warnings and Precautions (5.5)].

Ocular Toxicities

Advise patients that MEKINIST can cause severe visual disturbances that can lead to blindness and to contact their healthcare provider if they experience any changes in their vision [see Warnings and Precautions (5.6)].

Interstitial Lung Disease/Pneumonitis

Advise patients that MEKINIST can cause ILD (or pneumonitis). Advise patients to contact their healthcare provider as soon as possible if they experience signs, such as cough or dyspnea [see Warnings and Precautions (5.7)].

Serious Febrile Reactions

Advise patients that MEKINIST administered with dabrafenib can cause serious febrile reactions. Instruct patients to contact their healthcare provider if they develop a fever while taking MEKINIST with dabrafenib [see Warnings and Precautions (5.8)].

Serious Skin Toxicities

Advise patients that MEKINIST can cause serious skin toxicities, which may require hospitalization, and to contact their healthcare provider for progressive or intolerable rash. Advise patients to contact their healthcare provider immediately if they develop signs and symptoms of a severe skin reaction [see Warnings and Precautions (5.9)].

Hypertension

Advise patients that MEKINIST can cause hypertension and that they need to undergo blood pressure monitoring and to contact their healthcare provider if they develop symptoms of hypertension, such as severe headache, blurry vision, or dizziness [see Adverse Reactions (6.1)].

Diarrhea

Advise patients that MEKINIST often causes diarrhea which may be severe in some cases. Inform patients of the need to contact their healthcare provider if severe diarrhea occurs during treatment [see Adverse Reactions (6.1)].

Embryo-Fetal Toxicity

- Advise pregnant women and males of reproductive potential of the potential risk to a fetus [see Warnings and Precautions (5.13), Use in Specific Populations (8.1, 8.3)].
- Advise females to contact their healthcare provider of a known or suspected pregnancy.
- Advise females of reproductive potential to use effective contraception during treatment with MEKINIST and for 4 months after the last dose.
- Advise male patients with female partners of reproductive potential to use condoms during treatment with MEKINIST and for 4 months after the last dose.

Lactation

Advise women not to breastfeed during treatment with MEKINIST and for 4 months after the last dose [see Use in Specific Populations (8.2)].

Infertility

Advise females of reproductive potential of the potential risk for impaired fertility [see Use in Specific Populations (8.3)].

Administration

- Instruct patients to take MEKINIST tablets on an empty stomach (at least 1 hour before or 2 hours after a meal) [see Dosage and Administration (2.3)].
- When administering MEKINIST for oral solution as a single agent, instruct patients to take the oral solution with a low-fat meal or on an empty stomach [see Dosage and Administration (2.3)].
- When coadministering with dabrafenib, instruct patients to take the MEKINIST oral solution on an empty stomach (at least 1 hour before or 2 hours after a meal). Breastfeeding and/or baby formula may be given on demand if a pediatric patient is unable to tolerate the fasting conditions [see Dosage and Administration (2.3)].

THxID® BRAF assay is a trademark of bioMérieux.

Oncomine™ Dx Target Test is a trademark of Life Technologies Corporation, a part of Thermo Fisher Scientific Inc.

Distributed by:
Novartis Pharmaceuticals Corporation
East Hanover, New Jersey 07936

© Novartis

T2025-25

Patient Information

MEKINIST® (MEK-in-ist)
(trametinib)
tablets

MEKINIST® (MEK-in-ist)
(trametinib)
for oral solution

Important information: If your healthcare provider prescribes MEKINIST to be taken or given with dabrafenib, also read the Medication Guide that comes with dabrafenib.

What is the most important information I should know about MEKINIST?
MEKINIST may cause serious side effects, including:
Risk of new skin cancers. MEKINIST, when used with dabrafenib, may cause skin cancers, called cutaneous squamous cell carcinoma, keratoacanthoma, basal cell carcinoma, or melanoma.
Talk to your healthcare provider about your risk for these cancers.
Check your skin and tell your healthcare provider right away about any skin changes, including a:

- new wart
- skin sore or reddish bump that bleeds or does not heal
- change in size or color of a mole

Your healthcare provider should check your skin before treatment with MEKINIST and dabrafenib, every 2 months during treatment with MEKINIST and dabrafenib, and for up to 6 months after you stop taking MEKINIST and dabrafenib to look for any new skin cancers.
Your healthcare provider should also check for cancers that may not occur on the skin. Tell your healthcare provider about any new symptoms that develop during treatment with MEKINIST with dabrafenib.
See "What are the possible side effects of MEKINIST?" for more information about side effects.

What is MEKINIST?
MEKINIST is a prescription medicine used:

- alone or in combination with a medicine called dabrafenib to treat a type of skin cancer called melanoma:
  ○ that has spread to other parts of the body or cannot be removed by surgery, and
  ○ that has a certain type of abnormal “BRAF” gene.

MEKINIST should not be used to treat people who already have received a BRAF inhibitor for treatment of their melanoma, and it did not work or is no longer working.

- in combination with dabrafenib, to help prevent melanoma that has a certain type of abnormal “BRAF” gene from coming back after the cancer has been removed by surgery.

- in combination with dabrafenib to treat a type of lung cancer called non-small cell lung cancer (NSCLC):
  ○ that has spread to other parts of the body, and
  ○ that has a certain type of abnormal “BRAF” gene.

- in combination with dabrafenib to treat a type of thyroid cancer called anaplastic thyroid cancer (ATC):
  ○ that has spread to other parts of the body and you have no satisfactory treatment options, and
  ○ that has a certain type of abnormal “BRAF” gene.

- in combination with dabrafenib to treat solid tumors in adults and children 1 year and older:
  ○ that cannot be removed by surgery or have spread to other parts of the body, and that have gotten worse (progressed), and you have no satisfactory treatment options, and
  ○ that have a certain type of abnormal “BRAF” gene.

- in combination with dabrafenib to treat a type of brain tumor called glioma in children 1 year and older:
  ○ that is low-grade glioma (LGG), and
  ○ that have a certain type of abnormal “BRAF” gene, and
  ○ who require a medicine by mouth or injection (systemic therapy).

MEKINIST is not for use in treating people with colorectal cancer.
Your healthcare provider will perform a test to make sure that MEKINIST is right for you.
It is not known if MEKINIST used in combination with dabrafenib is safe and effective in children less than 1 year of age.
It is not known if MEKINIST used alone is safe and effective in children.

Before you take or give MEKINIST, tell your healthcare provider about all of your medical conditions, including if you:

- have had bleeding problems or blood clots
- have stomach problems
- have inflammation of the colon
- have heart problems
- have eye problems
- have lung or breathing problems
- have high blood pressure (hypertension)
- have liver or kidney problems
- have diabetes
- are pregnant or plan to become pregnant. MEKINIST can harm your unborn baby.
  Females who are able to become pregnant:
  ○ Your healthcare provider will do a test to see if you are pregnant before starting treatment with MEKINIST.
  ○ You should use effective birth control (contraception) during treatment with MEKINIST and for 4 months after your last dose of MEKINIST.
  ○ Talk to your healthcare provider about birth control methods that may be right for you during this time.
  ○ Tell your healthcare provider right away if you become pregnant or think you might be pregnant during treatment with MEKINIST.
  Males (including those who have had a vasectomy) with a female partner who is able to become pregnant:
  ○ Use condoms during sexual intercourse during treatment with MEKINIST and for at least 4 months after your last dose of MEKINIST.
- are breastfeeding or plan to breastfeed. It is not known if MEKINIST passes into your breast milk.
  ○ Do not breastfeed during treatment and for 4 months after your last dose of MEKINIST. Talk to your healthcare provider about the best way to feed your baby during this time.

Tell your healthcare provider about all the medicines you take, including prescription and over-the-counter medicines, vitamins, and herbal supplements.
Know the medicines you take. Keep a list of them to show your healthcare provider and pharmacist when you get a new medicine.

How should I take or give MEKINIST?

- Take or give MEKINIST exactly as your healthcare provider tells you to take or give it. Do not change your dose or stop MEKINIST unless your healthcare provider tells you.
- Your healthcare provider may change your dose of MEKINIST, temporarily stop, or completely stop your treatment with MEKINIST if you develop certain side effects.
- If you miss a dose of MEKINIST, take or give it as soon as you remember. Do not take or give a missed dose of MEKINIST if it is less than 12 hours before your next scheduled dose. Just skip the missed dose and take or give the next dose of MEKINIST at the regular time.
- If vomiting happens after taking or giving a dose of MEKINIST, do not take or give an additional dose. Take or give the next dose of MEKINIST at the regular time.

MEKINIST tablets:

- Take MEKINIST 1 time each day, at the same time each day, about every 24 hours.
- Take MEKINIST on an empty stomach (at least 1 hour before or 2 hours after a meal).
- Take MEKINIST tablets whole. Do not crush or break MEKINIST tablets.
- If MEKINIST tablets are prescribed for your child weighing at least 57 pounds (26 kg), your child’s healthcare provider will adjust their dose as your child grows.
- Tell your healthcare provider if you or your child is not able to swallow MEKINIST tablets whole.

MEKINIST for oral solution:

- MEKINIST for oral solution should only be given by a caregiver.
- If MEKINIST for oral solution is prescribed for your child, your child’s healthcare provider will adjust their dose as your child grows.
- See the “Instructions for Use” that comes with the medicine for instructions on how to correctly give a dose of MEKINIST.
- MEKINIST for oral solution can be given using an oral syringe or feeding tube (4 French gauge or larger).
- Give the MEKINIST oral solution 1 time each day, at the same time each day, about every 24 hours.
- Give the MEKINIST oral solution with a low-fat meal or on an empty stomach when giving MEKINIST alone.
- When giving MEKINIST in combination with dabrafenib, give the MEKINIST oral solution on an empty stomach (at least 1 hour before or 2 hours after a meal). If necessary, breastfeeding or baby formula may be given on demand.

What are the possible side effects of MEKINIST?
MEKINIST may cause serious side effects, including:

- See “What is the most important information I should know about MEKINIST?”
- bleeding problems. MEKINIST can cause serious bleeding problems, especially in your brain or stomach, that can lead to death. Call your healthcare provider and get medical help right away if you have any signs of bleeding, including:
  ○ headaches, dizziness, or feeling weak
  ○ cough up blood or blood clots
  ○ vomit blood or your vomit looks like “coffee grounds”
  ○ red or black stools that look like tar
- inflammation of the intestines, or tears (perforation) of the stomach or intestines. MEKINIST can cause inflammation of your intestines, or tears in the stomach or intestines that can lead to death. Tell your healthcare provider right away if you have any of the following symptoms:
  ○ bleeding. See “bleeding problems” above.
  ○ diarrhea (loose stools) or more bowel movements than usual
  ○ stomach-area (abdominal) pain or tenderness
  ○ fever
  ○ nausea
- blood clots. MEKINIST can cause blood clots in your arms or legs, which can travel to your lungs and can lead to death. Get medical help right away if you have the following symptoms:
  ○ chest pain
  ○ sudden shortness of breath or trouble breathing
  ○ pain in your legs with or without swelling
  ○ swelling in your arms or legs
  ○ a cool, pale arm or leg
- heart problems, including heart failure. Your healthcare provider should check your heart function before and during treatment with MEKINIST. Call your healthcare provider right away if you have any of the following signs and symptoms of a heart problem:
  ○ feeling like your heart is pounding, racing, or beating irregularly
  ○ shortness of breath
  ○ swelling of your ankles and feet
  ○ feeling lightheaded
- eye problems. MEKINIST can cause severe eye problems that might lead to blindness. Call your healthcare provider right away if you get these symptoms of eye problems:
  ○ blurred vision, loss of vision, or other vision changes
  ○ see color dots
  ○ halo (seeing blurred outline around objects)
  ○ eye pain, swelling, or redness
- lung or breathing problems. MEKINIST can cause lung or breathing problems. Tell your healthcare provider if you have any new or worsening symptoms of lung or breathing problems, including:
  ○ shortness of breath
  ○ cough
- fever. Fever is common during treatment with MEKINIST and dabrafenib, but it may also be serious. When taking MEKINIST with dabrafenib, fever may happen more often or may be more severe. In some cases, chills or shaking chills, too much fluid loss (dehydration), low blood pressure, dizziness, or kidney problems may happen with the fever.
  Call your healthcare provider right away if you get a fever during treatment with MEKINIST.
  Your healthcare provider may temporarily or permanently stop your treatment or change your dose of MEKINIST with dabrafenib if you have fevers. Your healthcare provider will treat you as needed for your fever and any signs and symptoms of infection and should check your kidney function during and after you have had severe fever.
- serious skin reactions. Skin rash is a common side effect of MEKINIST. MEKINIST can also cause other skin reactions. In some cases, these rashes and other skin reactions can be severe or serious and may need to be treated in a hospital or lead to death.
  Tell your healthcare provider if you get a skin rash or acne that bothers you or worsens.
  Tell your healthcare provider right away if you develop any new or worsening symptoms of a severe skin reaction, including:

○ blisters or peeling of your skin
○ mouth sores

○ blisters on your lips, or around your mouth or eyes
○ high fever or flu-like symptoms
○ enlarged lymph nodes

- increased blood sugar (hyperglycemia). Some people may develop high blood sugar or worsening diabetes during treatment with MEKINIST and dabrafenib. If you are diabetic, your healthcare provider should check your blood sugar levels closely during treatment with MEKINIST and dabrafenib. Your diabetes medicine may need to be changed. Tell your healthcare provider if you have any of the following symptoms of severe high blood sugar:
  ○ increased thirst
  ○ urinating more often than normal or urinating an increased amount of urine
- hemophagocytic lymphohistiocytosis (HLH). MEKINIST when taken or given with dabrafenib may increase the risk of a type of overactivity of the immune system (hemophagocytic lymphohistiocytosis) that can cause fever, swollen glands, bruising, or skin rash. If you experience a combination of these symptoms, call your healthcare provider right away.

The most common side effects of MEKINIST when taken alone include:

- rash
- diarrhea. Call your healthcare provider if you get severe diarrhea.
- swelling of the face, arms, or legs

The most common side effects of MEKINIST when taken with dabrafenib in people with melanoma that has spread to other parts of the body or cannot be removed by surgery include:

• fever

• diarrhea

• nausea

• vomiting

• rash

• high blood pressure (hypertension)

• chills

• swelling of the face, arms, or legs

The most common side effects of MEKINIST when taken with dabrafenib to help prevent melanoma from coming back after the cancer has been removed by surgery include:

• fever

• chills

• tiredness

• diarrhea

• nausea

• vomiting

• headache

• joint aches

• rash

• muscle aches

The most common side effects of MEKINIST when taken with dabrafenib in people with NSCLC include:

• fever

• rash

• tiredness

• swelling of your face, arms, and legs

• nausea

• chills

• vomiting

• bleeding

• diarrhea

• cough

• dry skin

• shortness of breath

• decreased appetite

The most common side effects of MEKINIST when taken with dabrafenib in adults with solid tumors that cannot be removed by surgery or have spread to other parts of the body include:

• fever

• bleeding

• tiredness

• cough

• nausea

• vomiting

• rash

• constipation

• chills

• diarrhea

• headache

• muscle and joint aches

• swelling of your arms and legs

The most common side effects of MEKINIST when given with dabrafenib in children 1 year of age and older with solid tumors that cannot be removed by surgery or have spread to other parts of the body include:

• fever

• acne

• rash

• headache

• vomiting

• stomach-area (abdominal) pain

• tiredness

• nausea

• dry skin

• bleeding

• cough

• constipation

• diarrhea

• skin infection around fingernails or toenails

The most common side effects of MEKINIST when given with dabrafenib in children 1 year of age and older with low-grade glioma include:

• fever

• diarrhea

• rash

• dry skin

• headache

• nausea

• vomiting

• bleeding

• muscle and bone pain

• stomach-area (abdominal) pain

• tiredness

• acne

MEKINIST can cause new or worsening high blood pressure (hypertension). Your healthcare provider should check your blood pressure during treatment with MEKINIST. Call your healthcare provider right away if you develop high blood pressure, your blood pressure worsens, or you have severe headache, lightheadedness, blurry vision, or dizziness.
MEKINIST may cause fertility problems in females. This could affect your ability to become pregnant. Talk to your healthcare provider if this is a concern for you.
These are not all the possible side effects of MEKINIST.
Call your healthcare provider for medical advice about side effects. You may report side effects to FDA at 1-800-FDA-1088.
You may also report side effects to Novartis Pharmaceuticals Corporation at 1-888-669-6682.

How should I store MEKINIST?
MEKINIST tablets:

- Store MEKINIST tablets at room temperature between 68°F to 77°F (20°C to 25°C).
- Keep MEKINIST tablets dry and away from moisture and light.
- The bottle of MEKINIST tablets contains a drying agent (desiccant packet) to help keep your medicine dry. Do not throw away (dispose of) the desiccant packet.
- Keep MEKINIST tablets in the original bottle. Do not place tablets in a pill box.
- Safely throw away MEKINIST tablets that are out of date or no longer needed.

MEKINIST for oral solution:

- Store MEKINIST for oral solution in the original amber bottle at room temperature below 77°F (25°C). Do not freeze.
- Keep MEKINIST for oral solution in the carton it comes in and away from direct moisture and light.
- Throw away unused MEKINIST for oral solution after the expiration or “discard after” date written on the amber bottle label.

Keep MEKINIST and all medicines out of the reach of children.

General information about the safe and effective use of MEKINIST
Medicines are sometimes prescribed for purposes other than those listed in a Patient Information leaflet. Do not use MEKINIST for a condition for which it was not prescribed. Do not give MEKINIST to other people, even if they have the same symptoms that you have. It may harm them. You can ask your healthcare provider or pharmacist for information about MEKINIST that is written for health professionals.

What are the ingredients in MEKINIST?
MEKINIST tablets:
Active ingredient: trametinib
Inactive ingredients:
Tablet Core: colloidal silicon dioxide, croscarmellose sodium, hypromellose, magnesium stearate (vegetable source), mannitol, microcrystalline cellulose, sodium lauryl sulfate.
Tablet Coating: hypromellose, iron oxide red (2 mg tablets), iron oxide yellow (0.5 mg tablets), polyethylene glycol, polysorbate 80 (2 mg tablets), titanium dioxide.
MEKINIST for oral solution:
Active ingredient: trametinib
Inactive ingredients: betadex sulfobutyl ether sodium, citric acid monohydrate, dibasic sodium phosphate, methylparaben, potassium sorbate, sucralose, and strawberry flavor.

Distributed by: Novartis Pharmaceuticals Corporation, East Hanover, New Jersey 07936

© Novartis

For more information, go to www.us.tafinlarmekinist.com or call 1-888-669-6682.

This Patient Information has been approved by the U.S. Food and Drug Administration.

Revised: March 2025

T2025-21

INSTRUCTIONS FOR USE
MEKINIST® (MEK-in-ist)
(trametinib)
for oral solution

This “Instructions for Use” contains information on how to give MEKINIST oral solution.

Important information you need to know before giving MEKINIST oral solution

- MEKINIST oral solution should only be given by a caregiver.
- Read this “Instructions for Use” carefully before you give MEKINIST oral solution for the first time and each time you get a refill. There may be new information.
- This “Instructions for Use” does not take the place of talking with your healthcare provider about your or your child’s medical condition and treatment.
- You will receive the MEKINIST oral solution in an amber-colored bottle that your pharmacist has already mixed.
  - If you receive MEKINIST as a powder, contact your healthcare provider or pharmacist right away. Do not mix the MEKINIST powder on your own.
  - Your pharmacist prepared the MEKINIST oral solution to an exact concentration. Do not add more water to the oral solution you receive from the pharmacy.
- Your healthcare provider or pharmacist should show the caregiver how to measure and give a dose of MEKINIST oral solution correctly. Always give MEKINIST oral solution exactly as your healthcare provider tells you to.
- If you have any questions about how to measure and give a dose of MEKINIST oral solution, talk to your healthcare provider or pharmacist.
- If at any time MEKINIST oral solution gets on your or your child’s skin, wash the area well with soap and water.
- If at any time MEKINIST oral solution gets in your or your child’s eyes, rinse the eyes well with cool water.
- Ask your healthcare provider or pharmacist about how to safely throw away (dispose of) MEKINIST oral solution.
- When MEKINIST is prepared as an oral solution, it can be used for 35 days. Throw away any remaining oral solution after 35 days.
- If you spill any MEKINIST oral solution, follow the instructions at the end of this "Instructions for Use" in the section called “How to clean up any spilled MEKINIST oral solution.”

The MEKINIST pack should contain:

Reusable oral syringe parts:

Storage of MEKINIST oral solution

- Store the amber bottle of MEKINIST oral solution at room temperature below 77°F (25°C).
- Do not freeze MEKINIST oral solution.
- Store the amber bottle of MEKINIST oral solution upright with the cap tightly closed.
- Keep MEKINIST oral solution in the carton it comes in and away from direct moisture and light.
- When MEKINIST is prepared as an oral solution, it can be used for 35 days. Throw away any remaining oral solution after 35 days.
- Do not use MEKINIST oral solution after the expiration or “discard after” date written or printed on the label by the pharmacist.
- Keep MEKINIST oral solution and all medicines out of the reach of children.

Storage of oral syringe

- Store the oral syringe with the MEKINIST oral solution.
- Keep oral syringe out of the reach of children.

Section A. Measuring and giving a dose of MEKINIST oral solution

- Gather your supplies:

To give a dose of MEKINIST oral solution, you will need:

- 1 bottle adapter (already inserted into the bottle neck)
- 1 amber bottle containing MEKINIST oral solution
- 1 reusable oral syringe

Call your healthcare provider or pharmacist if you do not have one or more of these items.

- If any of the MEKINIST oral solution comes into contact with your skin or eyes when you are following the steps below, follow the instructions in the section “Important information you need to know before giving MEKINIST oral solution” above.
- If any MEKINIST oral solution spills, follow the instructions in the section “How to clean up any spilled MEKINIST oral solution” at the end of this "Instructions for Use."

Step 1. Wash and dry your hands before measuring and giving a dose of MEKINIST oral solution.

Step 2. Place your supplies on a clean, flat work surface.

Step 3. Check if you have powder or solution in the amber bottle.

- If you have powder, do not give MEKINIST and contact your healthcare provider or pharmacist. Do not mix the MEKINIST powder on your own.
- If you have solution, continue to Step 4 below.
- Your pharmacist prepared the MEKINIST oral solution to an exact concentration. Do not add more water to the oral solution you receive from the pharmacy.

Step 4. Check the expiration or “discard after” date of the MEKINIST oral solution that is handwritten or printed on the amber bottle label.

- Do not give MEKINIST oral solution if the expiration or “discard after” date has passed or there is no date on the amber bottle label.
- Note: If you are unsure of the expiration or “discard after” date, contact your healthcare provider or pharmacist.

Step 5. Gently swirl the amber bottle for 30 seconds to mix the MEKINIST oral solution.

- If foam appears, put the amber bottle on a flat surface and let it sit there until the foam disappears.

Step 6. When the foam has disappeared inside the amber bottle, remove the child-resistant cap by pushing down on the cap and turning it in the direction of the arrow (counter-clockwise), as shown. Then place the amber bottle back on your flat work surface.

Step 7. Check if there is a bottle adapter already inserted in the bottle neck. Do not remove the bottle adapter. If not inserted, separate the bottle adapter from the oral syringe and insert it.
Contact your healthcare provider if you are unsure or the bottle adapter is missing.

Step 8. Next, pick up the oral syringe.
Push the plunger up into the oral syringe as far as it will go to remove all the air inside.

Step 9. Use one hand to hold the amber bottle containing the prepared MEKINIST oral solution steady.
With your other hand, insert the tip of the oral syringe into the opening of the bottle adapter.
Make sure the oral syringe is securely attached.
Important: Due to air pressure, the plunger may move by itself when you measure your dose during Step 10.
Hold the end of the plunger to prevent it from moving.

Step 10. Carefully turn the amber bottle upside down and pull down on the plunger to draw the MEKINIST oral solution into the oral syringe.
To measure your dose, keep the tip of the oral syringe facing up. Pull down on the plunger until the top of the black stopper lines up with your prescribed dose in mLs on the oral syringe barrel.
If large air bubbles appear in the oral syringe, push the MEKINIST oral solution back into the amber bottle and then pull down on the plunger again to draw up your dose.

Keep doing this until there are no large air bubbles present. Small air bubbles are okay.

Step 11. Continue to hold the plunger in place, and carefully turn the amber bottle upright. Put the amber bottle onto your flat work surface again.
While still holding the plunger and barrel, remove the oral syringe from the bottle by gently pulling straight up.

Check again to be sure that the top of the black stopper is at your prescribed dose. If not, repeat Steps 9, 10 and 11 again.
Note: Your dose may be different than the dose shown in this figure.
If you are giving a dose of MEKINIST oral solution by mouth, move to Step 12.
If you are giving a dose of MEKINIST oral solution through a feeding tube, go to Section B.

Step 12. Important: If giving a dose of MEKINIST oral solution to a child, make sure they are sitting upright. Place the tip of the oral syringe inside the mouth. The tip should touch the inside of either cheek.
Slowly push the plunger all the way down to give the full dose of MEKINIST oral solution.
Warning: Giving MEKINIST oral solution directly into the throat or pushing down on the plunger too fast may cause choking.

Step 13. Check to make sure that there is no MEKINIST oral solution left in the oral syringe.
If there is any MEKINIST oral solution left in the oral syringe, give it.
Note: If your dose in mLs is more than the oral syringe can hold, repeat Steps 8 through 14 until the total prescribed dose is given.

Step 14. When finished, close the amber bottle.
Do not remove the bottle adapter.
Place the cap back on the amber bottle and turn it in the direction of the arrow (clockwise), as shown, to close it.
Make sure the cap is securely attached onto the amber bottle.

Step 15. Clean the reusable oral syringe. See the instructions in Section C “Cleaning the reusable oral syringe.”

Section B. Giving a dose of MEKINIST oral solution through a feeding tube

This section is for use only if you are going to give a dose of MEKINIST oral solution through a feeding tube.
Before giving a dose of MEKINIST oral solution through a feeding tube, carefully read the following information, then move to Step 1.

- MEKINIST oral solution may be given through a feeding tube, as directed by your healthcare provider.
- Only use a nasogastric (NG) or gastric (G-tube) feeding tube with a size of 4 French gauge or larger.
- Always use the 20 mL oral syringe provided in this pack to give a dose of MEKINIST oral solution.
- You may need an ENFIT adapter (not included in this pack) to connect the 20 mL oral syringe to the feeding tube.

Step 1. Flush the feeding tube according to the manufacturer’s instructions right away before giving a dose of MEKINIST oral solution.

Step 2. Follow Steps 1 through 11 in Section A, then move to Step 3 in this section.

Step 3. Connect the 20 mL oral syringe containing MEKINIST oral solution to the feeding tube. You may need an ENFIT adapter to connect the oral syringe to the feeding tube.

Step 4. Apply steady pressure to the plunger to give the dose of MEKINIST oral solution through the feeding tube.

Step 5. Check to be sure that there is no MEKINIST oral solution left in the oral syringe.
If there is any MEKINIST oral solution left in the oral syringe, repeat Steps 3 through 5.

Step 6. Flush the feeding tube again according to the manufacturer’s instructions.

Step 7. Go to Section C for instructions on “Cleaning the reusable oral syringe.”

Section C. Cleaning the reusable oral syringe

Note: Clean the oral syringe separate from other kitchen items.

Step 1. Fill a glass with warm, soapy water.

Step 2. Place the tip of the oral syringe into the glass of warm, soapy water.
Pull up and then push down on the plunger to pull the soapy water in and out of the oral syringe 4 to 5 times.

Step 3. Remove the plunger from the barrel.

Step 4. Rinse the glass, plunger, and barrel under warm tap water.

Step 5. Leave the oral syringe plunger and barrel on a clean paper towel to air dry. When your oral syringe is dry, store it with the amber bottle of MEKINIST oral solution.
Always keep the oral syringe out of the reach of children.
Note: Use a new oral syringe for each new amber bottle of MEKINIST oral solution.

How to throw away MEKINIST oral solution that is expired or no longer needed, or old oral syringes

- Throw away unused MEKINIST oral solution into the trash. Do not pour MEKINIST oral solution down the drain.
- Ask your healthcare provider or pharmacist about how to safely throw away MEKINIST oral solution if you are not sure.
- Use a new oral syringe for each new amber bottle of MEKINIST oral solution. Throw away the old oral syringe into the trash.
- Ask your healthcare provider or pharmacist how to safely throw away the oral syringe if you are not sure.

How to clean up any spilled MEKINIST oral solution

If you accidentally spill any MEKINIST oral solution, clean up the spill as follows:
1. Put on plastic gloves.
2. Soak up the spilled MEKINIST oral solution completely using an absorbent material, such as paper towels.
3. Place the used absorbent material into a sealable plastic bag, such as a food storage bag.
4. Wipe all surfaces exposed to MEKINIST oral solution with alcohol wipes or pour rubbing alcohol onto a paper towel and then wipe the exposed surfaces with the paper towel.
5. Place the bag, gloves and used alcohol wipes or paper towel into another second plastic bag and seal.
6. Throw away the bags into the trash.
7. Wash your hands well with soap and water.

Distributed by:
Novartis Pharmaceuticals Corporation
East Hanover, New Jersey 07936
© Novartis

This Instructions for Use has been approved by the U.S. Food and Drug Administration.

Revised: March 2025

T2025-13

PRINCIPAL DISPLAY PANEL

NDC 0078-1105-15

Mekinist® (trametinib) Tablets

0.5 mg*

Rx only

30 Tablets

NOVARTIS

PRINCIPAL DISPLAY PANEL

NDC 0078-1112-15

Mekinist® (trametinib) Tablets

2 mg*

Rx only

30 Tablets

NOVARTIS

PRINCIPAL DISPLAY PANEL

NDC 0078-1161-47

Rx only

Mekinist®
(trametinib)
for Oral Solution

0.05 mg per mL*

90 mL (when reconstituted)

To Pharmacist: Reconstitute before
dispensing*. Dispense with the enclosed
Patient Information and Instructions
for Use.

For administration by caregivers only.

Discard any unused solution 35 days after reconstitution.

NOVARTIS